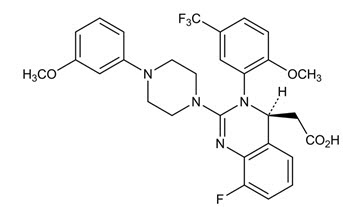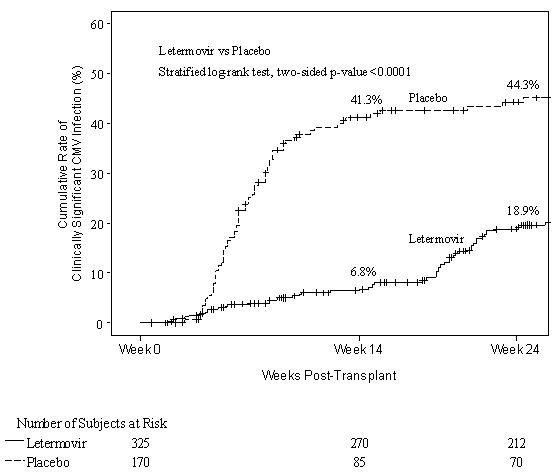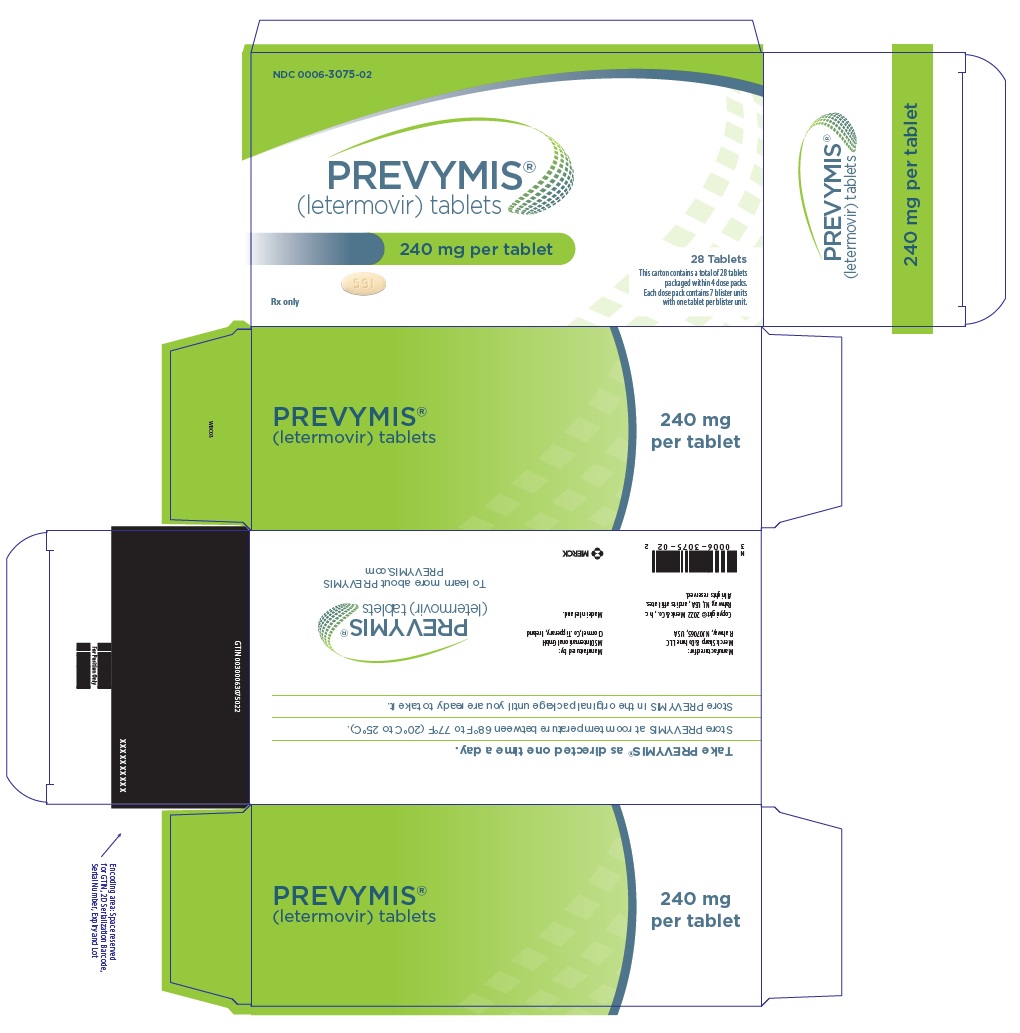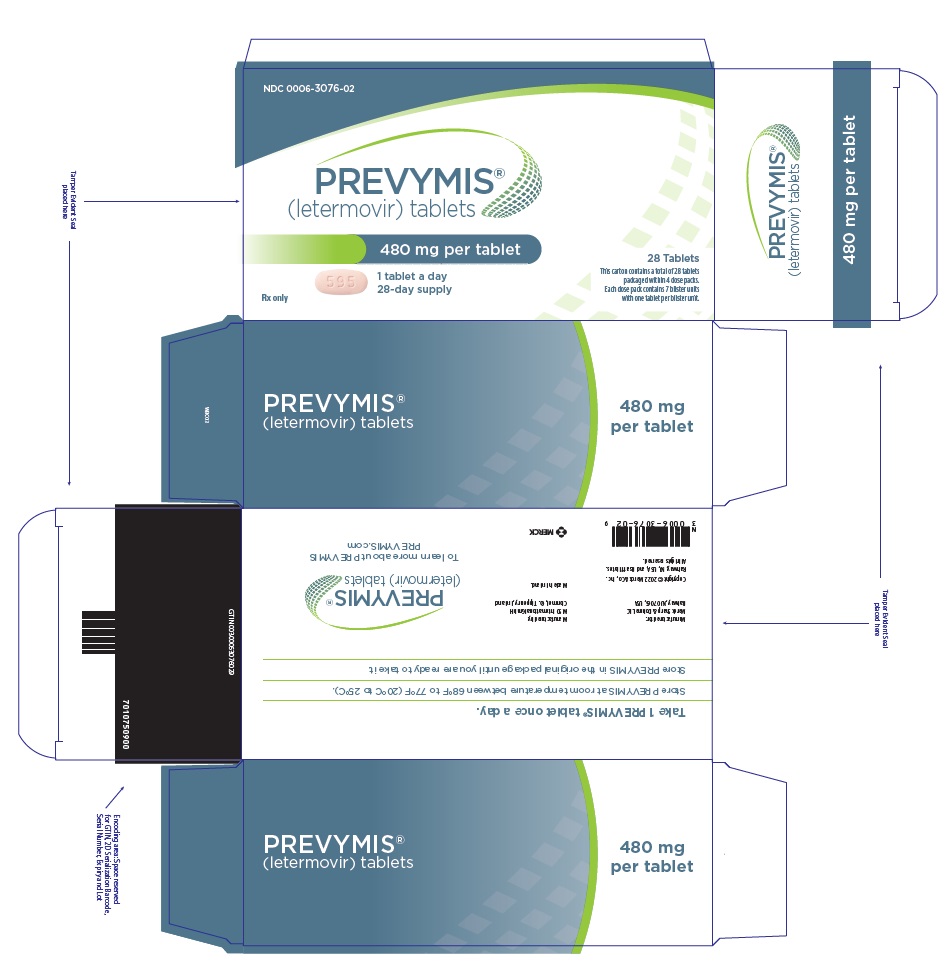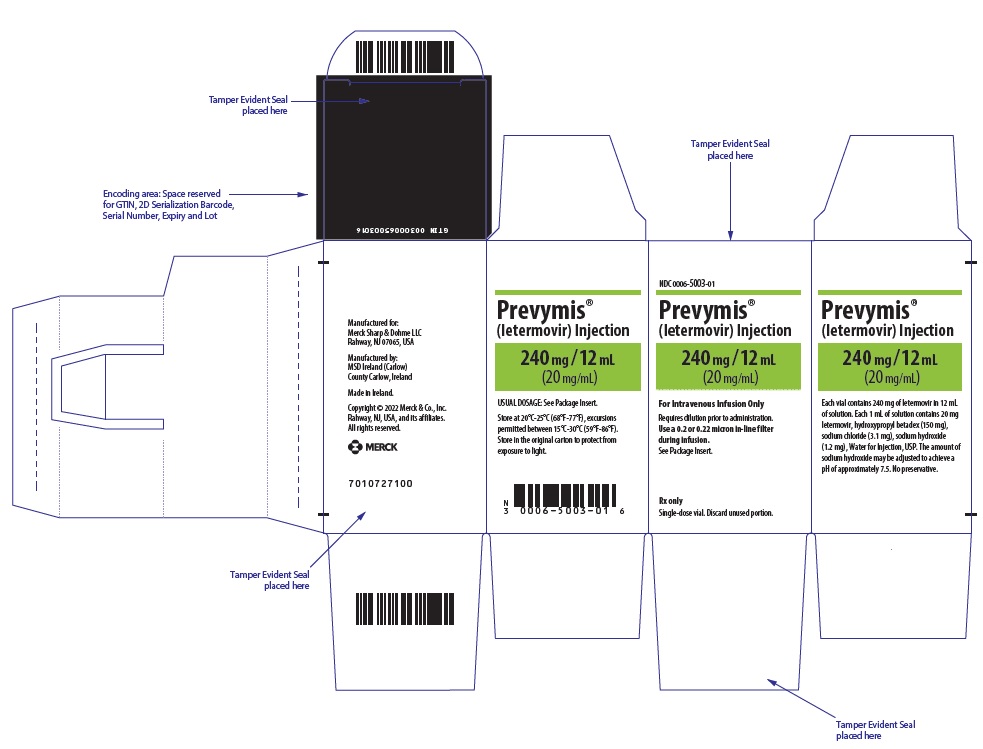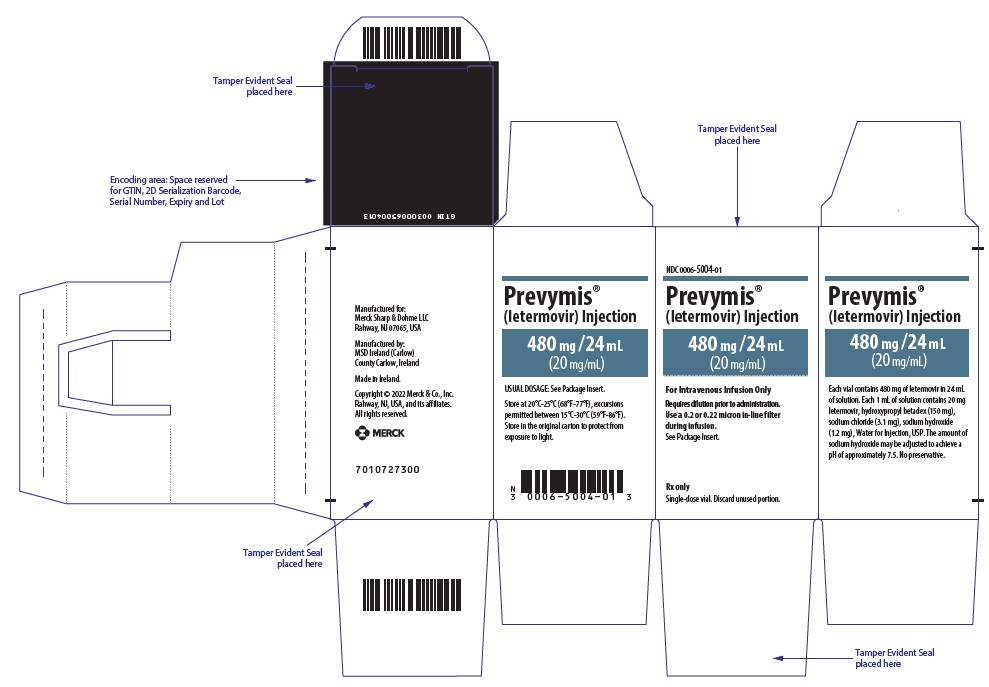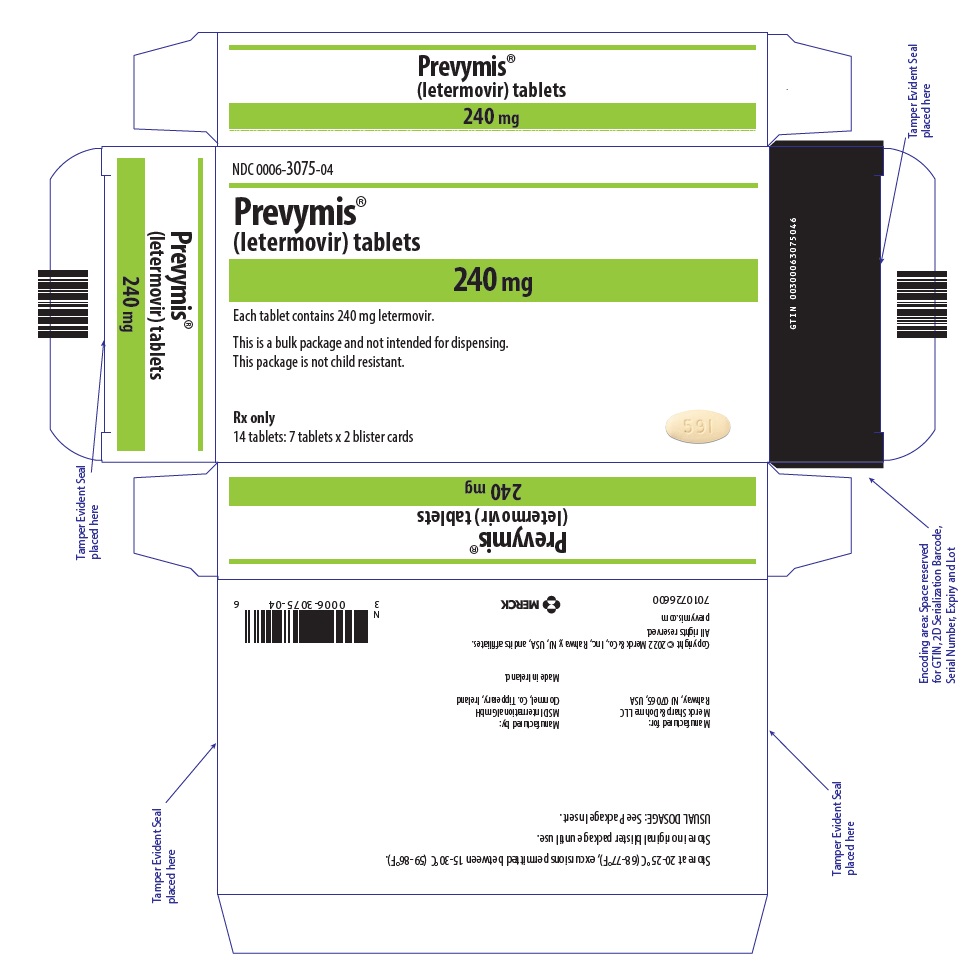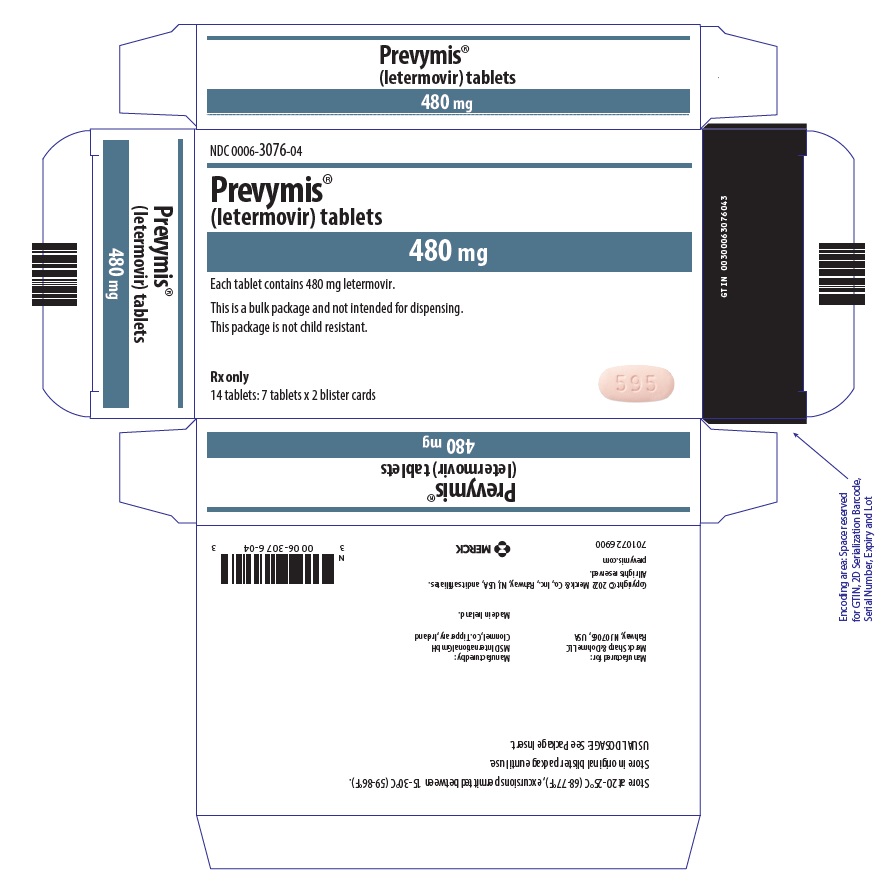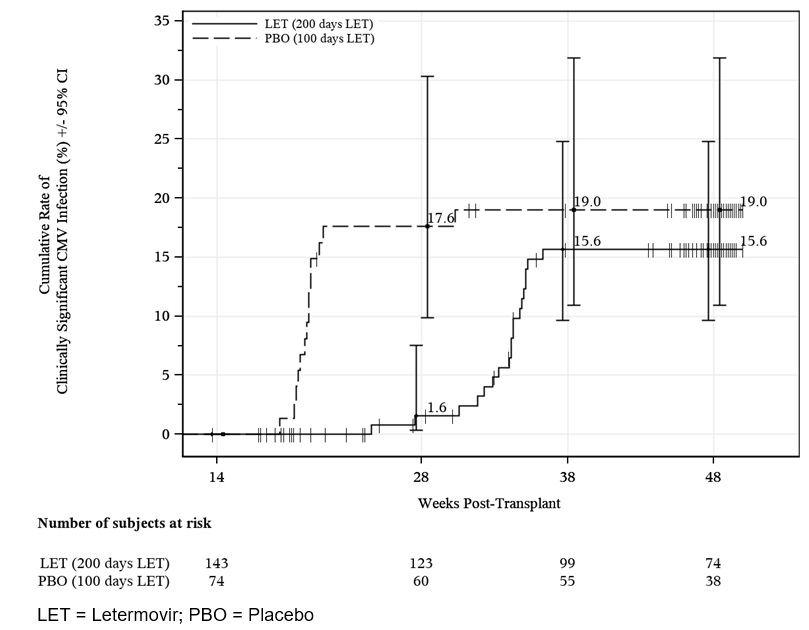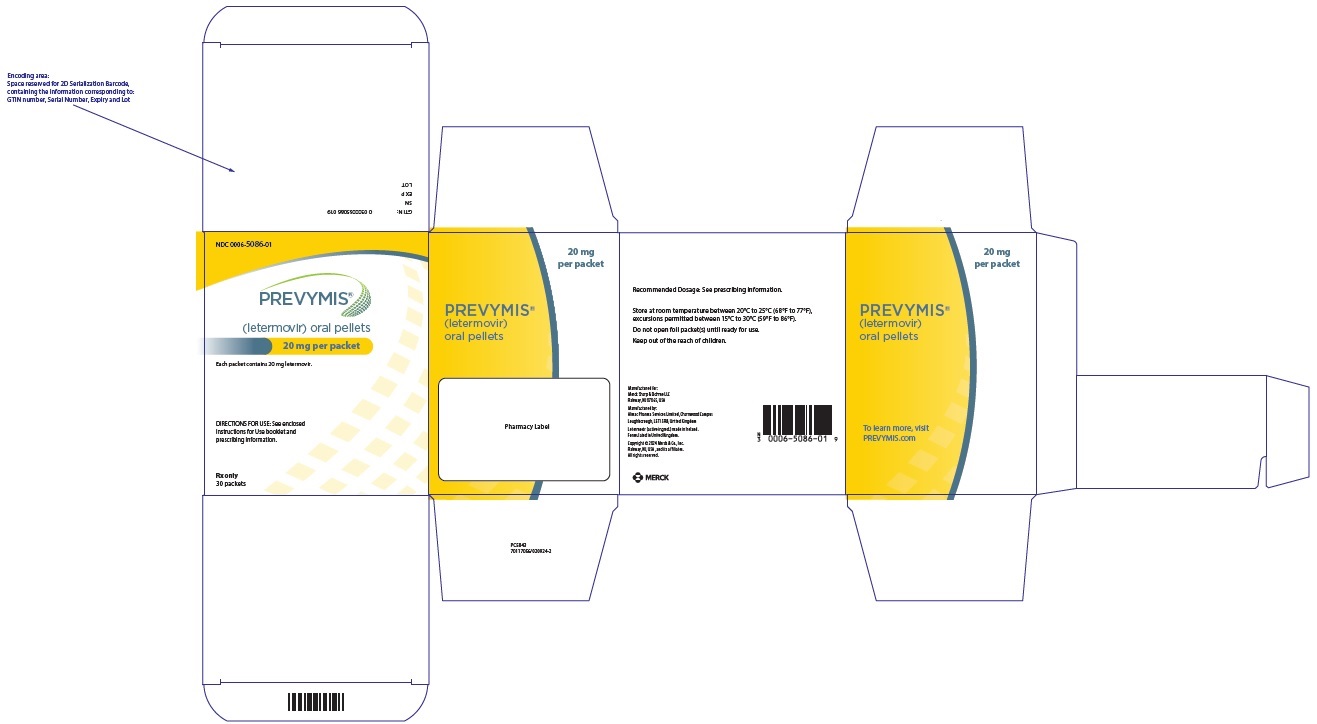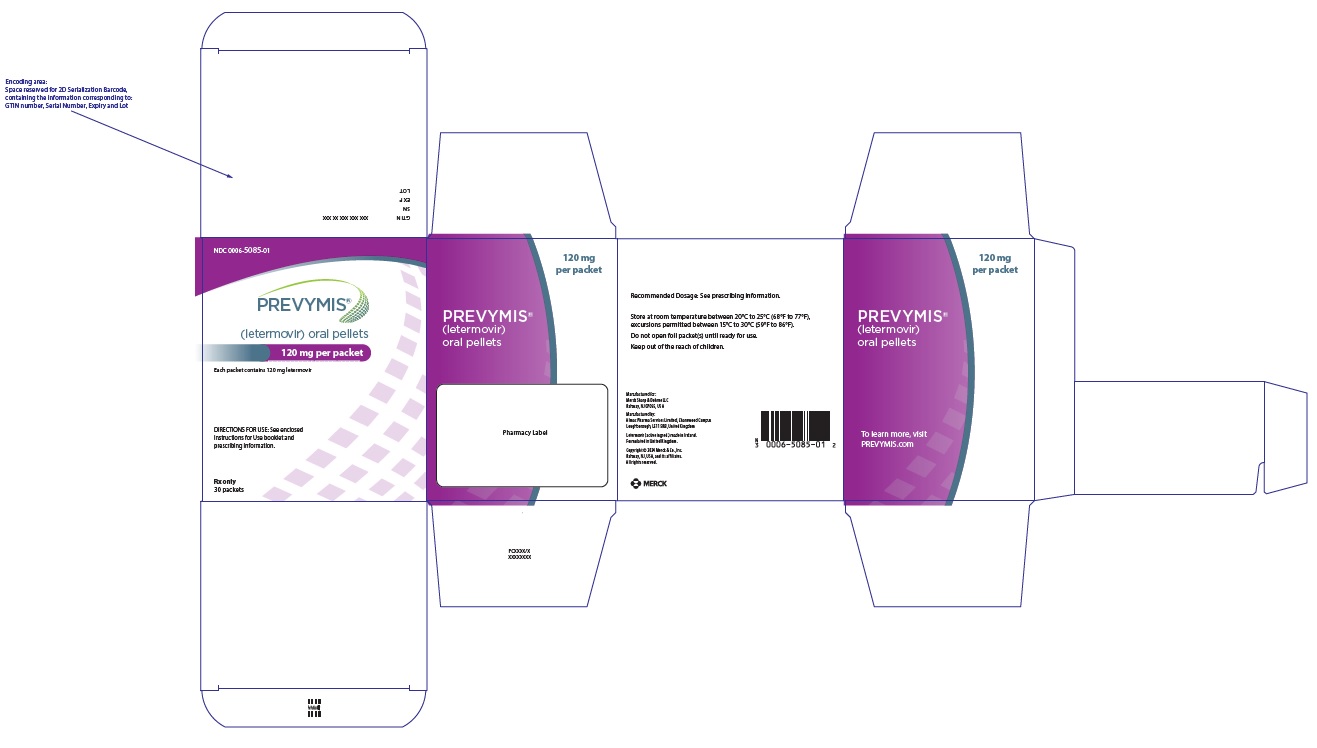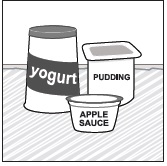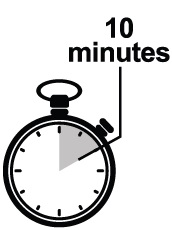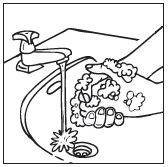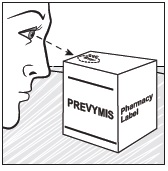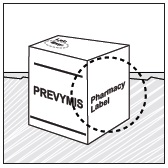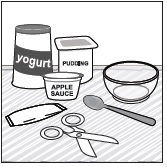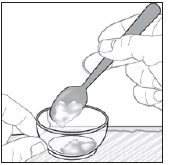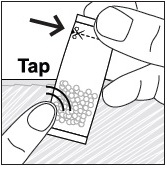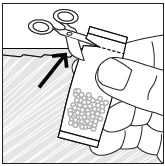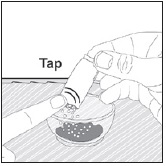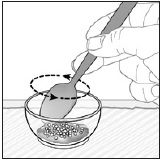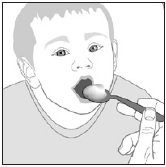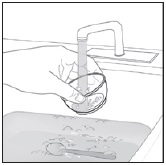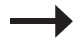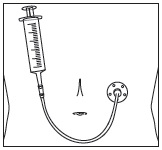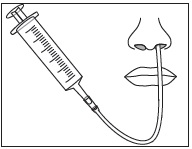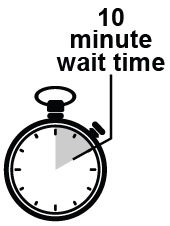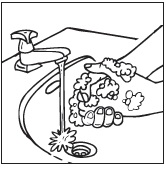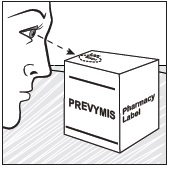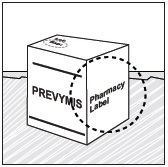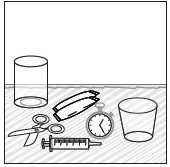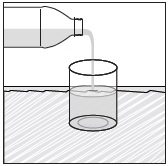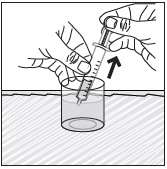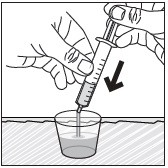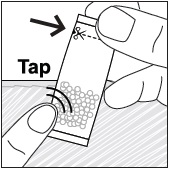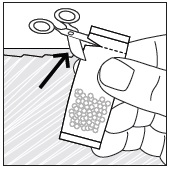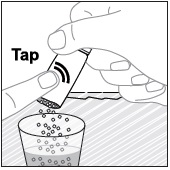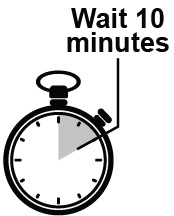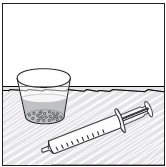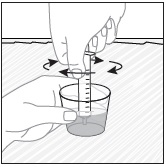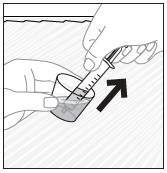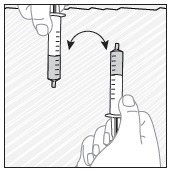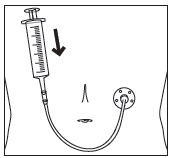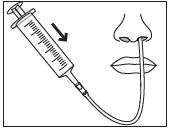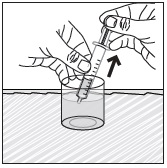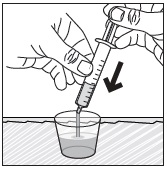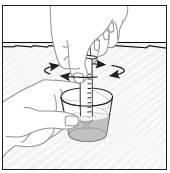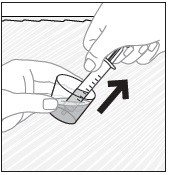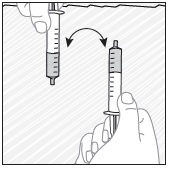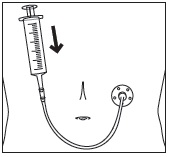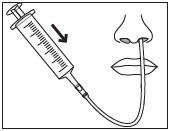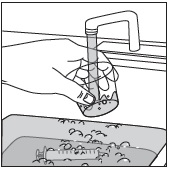 DRUG LABEL: PREVYMIS
NDC: 0006-3075 | Form: TABLET, FILM COATED
Manufacturer: Merck Sharp & Dohme LLC
Category: prescription | Type: HUMAN PRESCRIPTION DRUG LABEL
Date: 20260114

ACTIVE INGREDIENTS: LETERMOVIR 240 mg/1 1
INACTIVE INGREDIENTS: MICROCRYSTALLINE CELLULOSE; CROSCARMELLOSE SODIUM; POVIDONE K25; SILICON DIOXIDE; MAGNESIUM STEARATE; LACTOSE MONOHYDRATE; HYPROMELLOSE 2910 (6 MPA.S); HYPROMELLOSE 2910 (15 MPA.S); TITANIUM DIOXIDE; TRIACETIN; FERRIC OXIDE YELLOW; CARNAUBA WAX

HIGHLIGHTS OF PRESCRIBING INFORMATION

These highlights do not include all the information needed to use PREVYMIS safely and effectively. See full prescribing information for PREVYMIS.
PREVYMIS® (letermovir) tablets, for oral use
PREVYMIS® (letermovir) oral pellets
PREVYMIS® (letermovir) injection, for intravenous use
Initial U.S. Approval: 2017

1 INDICATIONS AND USAGE

PREVYMIS is a CMV DNA terminase complex inhibitor indicated for:

- Prophylaxis of cytomegalovirus (CMV) infection and disease in adult and pediatric patients 6 months of age and older and weighing at least 6 kg who are CMV-seropositive recipients [R+] of an allogeneic hematopoietic stem cell transplant (HSCT). (1.1)
- Prophylaxis of CMV disease in adult and pediatric patients 12 years of age and older and weighing at least 40 kg who are kidney transplant recipients at high risk (Donor CMV seropositive/Recipient CMV seronegative [D+/R-]). (1.2)

2 DOSAGE AND ADMINISTRATION

- Adult and Pediatric Patients 12 Years of Age and Older and Weighing at least 30 kg Who Are HSCT Recipients or Adult and Pediatric Patients 12 Years of Age and Older and Weighing at least 40 kg Who Are Kidney Transplant Recipients:
  - HSCT: 480 mg administered once daily orally or as an intravenous (IV) infusion over 1 hour through 100 days post-HSCT. In patients at risk for late CMV infection and disease, PREVYMIS may be continued through 200 days post-HSCT. (2.1, 2.3)
  - Kidney Transplant: 480 mg administered once daily orally or as an IV infusion over 1 hour through 200 days post-transplant. (2.1, 2.3)
- Pediatric Patients 6 Months to Less than 12 Years of Age or 12 Years of Age and Older and Weighing Less than 30 kg Who Are HSCT Recipients:
  - HSCT: Dosing based on weight administered once daily orally or as an IV infusion over 1 hour through 100 days post-HSCT. In patients at risk for late CMV infection and disease, PREVYMIS may be continued through 200 days post-HSCT. (2.1, 2.5)
- PREVYMIS injection must be diluted prior to administration. (2.1)
- PREVYMIS injection must be administered through a sterile 0.2 micron or 0.22 micron polyethersulfone (PES) in-line filter. (2.1, 2.10)
- Following the completion of PREVYMIS prophylaxis, monitoring for CMV reactivation in HSCT recipients is recommended. (2.2)
- Dosage Adjustment: If PREVYMIS is co-administered with cyclosporine, the dosage of PREVYMIS should be decreased to 240 mg once daily in adult and pediatric patients 12 years of age and older. (2.4) If PREVYMIS is co-administered with cyclosporine in pediatric patients less than 12 years of age, dose adjustment may be required. (2.6)
- Instructions for Use should be followed for preparation and administration of PREVYMIS oral pellets. (2.9)
- Do not use PREVYMIS injection with IV bags and infusion set materials containing the plasticizer diethylhexyl phthalate (DEHP). (2.10, 2.13)

3 DOSAGE FORMS AND STRENGTHS

- Tablet: 240 mg; 480 mg (3)
- Oral Pellets: 20 mg or 120 mg per packet (3)
- Injection: 240 mg/12 mL (20 mg/mL) or 480 mg/24 mL (20 mg/mL) in a single-dose vial (3)

4 CONTRAINDICATIONS

PREVYMIS is contraindicated with:

- Pimozide. (4)
- Ergot Alkaloids. (4)
- Pitavastatin and simvastatin when co-administered with cyclosporine. (4)

5 WARNINGS AND PRECAUTIONS

- Risk of Adverse Reactions or Reduced Therapeutic Effect Due to Drug Interactions: The concomitant use of PREVYMIS with certain drugs may result in potentially significant drug interactions, some of which may lead to adverse reactions (PREVYMIS or concomitant drugs) or reduced therapeutic effect of PREVYMIS or the concomitant drug. Consult the full prescribing information for contraindications and dosage recommendations for concomitant drugs. (4, 5.1, 7.1, 7.2, 7.3)
- Risks Associated with Hydroxypropyl Betadex Excipient in Intravenous Formulation: Intravenous formulation of PREVYMIS contains the excipient hydroxypropyl betadex. PREVYMIS injection should be used only in patients unable to take oral therapy. If possible, intravenous administration should not exceed 4 weeks. In patients with renal impairment, accumulation of hydroxypropyl betadex may occur. Animal studies have shown the potential for hydroxypropyl betadex to cause ototoxicity. (5.2, 8.6, 13.2)

6 ADVERSE REACTIONS

- Adult HSCT Patients: Most common adverse events (occurring in at least 10% of subjects in the PREVYMIS group and at a frequency at least 2% greater than placebo) are nausea, diarrhea, vomiting, peripheral edema, cough, headache, fatigue, and abdominal pain. (6.1)
- Adult Kidney Transplant Patients: Most common adverse event (occurring in at least 10% of subjects in the PREVYMIS group and at a frequency greater than valganciclovir) is diarrhea. (6.1)
- Pediatric Patients: Adverse events in pediatric patients are similar to adults. (6.1)

To report SUSPECTED ADVERSE REACTIONS, contact Merck Sharp & Dohme LLC at 1-877-888-4231 or FDA at 1-800-FDA-1088 or www.fda.gov/medwatch .

7 DRUG INTERACTIONS

- Dosage Adjustment: If PREVYMIS is co-administered with cyclosporine, the dosage of PREVYMIS should be decreased to 240 mg once daily in adult and pediatric patients 12 years of age and older. (2.4) If PREVYMIS is co-administered with cyclosporine in pediatric patients less than 12 years of age, dose adjustment may be required. (2.6)
- Co-administration of PREVYMIS may alter the plasma concentrations of other drugs and other drugs may alter the plasma concentrations of PREVYMIS. Consult the full prescribing information prior to and during treatment for potential drug interactions. (2.4, 2.6, 4, 5.1, 7.1, 7.2, 7.3, 7.4, 12.3)

8 USE IN SPECIFIC POPULATIONS

- Renal Impairment: Closely monitor serum creatinine levels in patients with CLcr less than 50 mL/min using PREVYMIS injection. (8.6)
- Hepatic Impairment: PREVYMIS is not recommended for patients with severe (Child-Pugh C) hepatic impairment. (8.7)

FULL PRESCRIBING INFORMATION

1 INDICATIONS AND USAGE

1.1 CMV Prophylaxis in Hematopoietic Stem Cell Transplant (HSCT) Recipients

PREVYMIS® is indicated for prophylaxis of cytomegalovirus (CMV) infection and disease in adult and pediatric patients 6 months of age and older and weighing at least 6 kg who are CMV-seropositive recipients [R+] of an allogeneic hematopoietic stem cell transplant (HSCT).

1.2 CMV Prophylaxis in Kidney Transplant Recipients

PREVYMIS is indicated for prophylaxis of CMV disease in adult and pediatric patients 12 years of age and older and weighing at least 40 kg who are kidney transplant recipients at high risk (Donor CMV seropositive/Recipient CMV seronegative [D+/R-]).

2 DOSAGE AND ADMINISTRATION

2.1 Important Dosing and Administration Information

- PREVYMIS is available in 3 dosage forms:
  - PREVYMIS Tablets
    - Administer orally with or without food.
    - Swallow tablets whole.
  - PREVYMIS Oral Pellets
    - Administer orally mixed with soft food or via nasogastric tube (NG tube) or gastric tube (G tube) [see Dosage and Administration (2.9)].
    - Do not crush or chew.
  - PREVYMIS Injection
    - PREVYMIS injection must be diluted prior to administration.
    - Administer PREVYMIS through a sterile 0.2 micron or 0.22 micron polyethersulfone (PES) in-line filter.
    - Administer by intravenous infusion via a peripheral catheter or central venous line at a constant rate over 1 hour.
    - Do not administer as an intravenous bolus injection.
    - PREVYMIS injection, which contains hydroxypropyl betadex, should be used only in patients unable to take oral therapy. Patients should be switched to oral PREVYMIS as soon as they are able to take oral medications. If possible, intravenous administration should not exceed 4 weeks [see Warnings and Precautions (5.2)].
- No dosage adjustment is necessary when switching formulations in adult and pediatric patients 12 years of age and older [see Dosage and Administration (2.3)].
- Dosage adjustment may be necessary for pediatric patients less than 12 years of age when switching between oral and intravenous formulations (see Table 1 and Table 2) [see Dosage and Administration (2.5)].

2.2 Patient Monitoring

Following the completion of PREVYMIS prophylaxis, monitoring for CMV reactivation in HSCT recipients is recommended [see Clinical Studies (14.2)].

2.3 Recommended Dosage for Adult and Pediatric Patients 12 Years of Age and Older Who Are HSCT or Kidney Transplant Recipients

HSCT: Adult and Pediatric Patients 12 Years of Age and Older and Weighing at least 30 kg

The recommended dosage of PREVYMIS is 480 mg administered orally or intravenously once daily. When PREVYMIS is administered orally, the recommended dosage is one 480 mg tablet once daily or two 240 mg tablets once daily. Four 120 mg packets of oral pellets once daily can be used for patients who cannot swallow tablets [see Dosage and Administration (2.9)]. For preparation and administration instructions of intravenous dosing refer to instructions in subsection 2.10 [see Dosage and Administration (2.10)]. For pediatric patients less than 12 years of age or weighing less than 30 kg, refer to weight-based dosing in Table 1 and Table 2 [see Dosage and Administration (2.5)].

Initiate PREVYMIS between Day 0 and Day 28 post-HSCT (before or after engraftment) and continue through Day 100 post-HSCT. In patients at risk for late CMV infection and disease, PREVYMIS may be continued through Day 200 post-HSCT [see Clinical Studies (14.2)].

Dosage of PREVYMIS should be adjusted when co-administered with cyclosporine [see Dosage and Administration (2.4)].

Kidney Transplant: Adult and Pediatric Patients 12 Years of Age and Older and Weighing at least 40 kg

The recommended dosage of PREVYMIS is 480 mg administered orally or intravenously once daily. When PREVYMIS is administered orally, the recommended dosage is one 480 mg tablet once daily or two 240 mg tablets once daily. Four 120 mg packets of oral pellets once daily can be used for patients who cannot swallow tablets [see Dosage and Administration (2.9)]. For preparation and administration instructions of intravenous dosing refer to instructions in subsection 2.10 [see Dosage and Administration (2.10)].

Initiate PREVYMIS between Day 0 and Day 7 post-transplant and continue through Day 200 post-transplant.

Dosage of PREVYMIS should be adjusted when co-administered with cyclosporine [see Dosage and Administration (2.4)].

2.4 Dosage Adjustment When Co-administered with Cyclosporine for Adult and Pediatric Patients 12 Years of Age and Older Who Are HSCT or Kidney Transplant Recipients

- If oral or intravenous PREVYMIS is co-administered with cyclosporine, the dosage of PREVYMIS should be decreased to 240 mg once daily in the following populations [see Drug Interactions (7.1, 7.2, 7.3) and Clinical Pharmacology (12.3)]:
  - HSCT: adult and pediatric patients 12 years of age and older and weighing at least 30 kg
    or
  - Kidney transplant: adult and pediatric patients 12 years of age and older and weighing at least 40 kg.
- If cyclosporine is initiated after starting PREVYMIS, the next dose of PREVYMIS should be decreased to 240 mg once daily.
- If cyclosporine is discontinued after starting PREVYMIS, the next dose of PREVYMIS should be increased to 480 mg once daily.
- If cyclosporine dosing is interrupted due to high cyclosporine levels, no dose adjustment of PREVYMIS is needed.

2.5 Recommended Dosage for Pediatric Patients 6 Months to Less than 12 Years of Age or 12 Years of Age and Older and Weighing Less than 30 kg Who Are HSCT Recipients

The recommended dosages of PREVYMIS for pediatric HSCT recipients 6 months to less than 12 years of age are based on weight and shown in Table 1 (tablets or oral pellets) and Table 2 (injection) [see Clinical Pharmacology (12.3)]. PREVYMIS can be administered orally (tablet or pellet) or intravenously once daily. Dosage adjustment may be necessary for pediatric patients less than 12 years of age when switching between oral and intravenous formulations (see Table 1 and Table 2).

Initiate PREVYMIS between Day 0 and Day 28 post-HSCT (before or after engraftment) and continue through Day 100 post-HSCT. In patients at risk for late CMV infection and disease, PREVYMIS may be continued through Day 200 post-HSCT [see Clinical Studies (14.2)].

Table 1: Recommended Daily Oral Dosage of PREVYMIS in Pediatric HSCT Recipients 6 Months to Less than 12 Years of Age or 12 Years of Age and Older and Weighing Less than 30 kg
Body Weight | Daily Oral Dose | Tablets | Oral Pellets
30 kg and above | 480 mg | One 480 mg tablet or Two 240 mg tablets | Four 120 mg packets of oral pellets
15 kg to less than 30 kg | 240 mg | One 240 mg tablet | Two 120 mg packets of oral pellets
7.5 kg to less than 15 kg | 120 mg | Not recommended | One 120 mg packet of oral pellets
6 kg to less than 7.5 kg | 80 mg | Not recommended | Four 20 mg packets of oral pellets

Table 2: Recommended Daily IV Dosage of PREVYMIS in Pediatric HSCT Recipients 6 Months to Less than 12 Years of Age or 12 Years of Age and Older and Weighing Less than 30 kg
Body Weight | Daily IV [Refer to Subsection 2.10 for intravenous preparation and administration dosing instructions] Dose
30 kg and above | 480 mg
15 kg to less than 30 kg | 120 mg
7.5 kg to less than 15 kg | 60 mg
6 kg to less than 7.5 kg | 40 mg

2.6 Dosage Adjustment When Co-administered with Cyclosporine for Pediatric Patients 6 Months to Less than 12 Years of Age or 12 Years of Age and Older and Weighing Less than 30 kg Who Are HSCT Recipients

If oral or intravenous PREVYMIS is co-administered with cyclosporine in pediatric HSCT recipients 6 months to less than 12 years of age, the dosage of PREVYMIS may require adjustment as shown in Table 3 [see Drug Interactions (7.1, 7.2, 7.3) and Clinical Pharmacology (12.3)].

- If cyclosporine is initiated after starting PREVYMIS, the next dose of PREVYMIS should be the daily oral or intravenous dose co-administered with cyclosporine (Table 3)
- If cyclosporine is discontinued after starting PREVYMIS, the next dose of PREVYMIS should be the daily oral or intravenous dose administered without cyclosporine (Table 1 or Table 2)
- If cyclosporine dosing is interrupted due to high cyclosporine levels, no dose adjustment of PREVYMIS is needed.

Table 3: Recommended Dosage of PREVYMIS when Co-administered with Cyclosporine in Pediatric HSCT Recipients 6 Months to Less than 12 Years of Age or 12 Years of Age and Older and Weighing Less than 30 kg
Body Weight | Daily Oral Dose | Tablets | Oral Pellets | Daily IV [Refer to Subsection 2.10 for intravenous preparation and administration dosing instructions] Dose
30 kg and above | 240 mg | One 240 mg tablet | Two 120 mg packets of oral pellets | 240 mg
15 kg to less than 30 kg | 120 mg | Not recommended | One 120 mg packet of oral pellets | 120 mg
7.5 kg to less than 15 kg | 60 mg | Not recommended | Three 20 mg packets of oral pellets | 60 mg
6 kg to less than 7.5 kg | 40 mg | Not recommended | Two 20 mg packets of oral pellets | 40 mg

2.7 Use in Patients with Renal Impairment

- For adult patients with creatinine clearance (CLcr) greater than 10 mL/min and pediatric patients with a similar degree of renal impairment (based on age-appropriate assessment of renal function), no dosage adjustment of PREVYMIS is required based on renal impairment [see Use in Specific Populations (8.6), and Clinical Pharmacology (12.3)].
- There are insufficient data in adult patients with CLcr 10 mL/min or less or in patients on dialysis or in pediatric patients with a similar degree of renal impairment (based on age-appropriate assessment of renal function) to make PREVYMIS dosing recommendations.
- In adult patients with CLcr less than 50 mL/min and in pediatric patients with a similar degree of renal impairment (based on age-appropriate assessment of renal function) receiving PREVYMIS injection, accumulation of the intravenous vehicle, hydroxypropyl betadex, may occur. Closely monitor serum creatinine levels in these patients [see Warnings and Precautions (5.2)].

2.8 Use in Patients with Hepatic Impairment

No dosage adjustment of PREVYMIS is required for patients with mild (Child-Pugh Class A) or moderate (Child-Pugh Class B) hepatic impairment. PREVYMIS is not recommended for patients with severe (Child-Pugh Class C) hepatic impairment [see Use in Specific Populations (8.7)].

2.9 Preparation and Administration of Oral Pellets

PREVYMIS oral pellets can be administered:

- orally after mixing with soft food or
- via NG tube or G tube.

Preparation and Administration Mixed with Soft Food

- See Instructions for Use for details on the preparation and administration of PREVYMIS oral pellets mixed with soft food.
- Do not crush or chew PREVYMIS oral pellets.
- Mix PREVYMIS oral pellets with 1 to 3 teaspoons of soft food (such as applesauce, yogurt, or pudding) that is at or below room temperature. Do not use hot food.
- Administer entire mixture within 10 minutes of mixing PREVYMIS oral pellets with the soft food.

Preparation and Administration via NG Tube or G Tube

See Instructions for Use, Table 4 (NG tube) and Table 5 (G tube) for details on the preparation and administration of PREVYMIS oral pellets via NG tube or G tube.

1. Pour PREVYMIS oral pellets into a medicine cup containing room temperature water (see Initial Volume in Table 4 and Table 5). Do not mix PREVYMIS oral pellets with hot or cold (refrigerated) water.
2. Wait 10 minutes. Do not shake or swirl the medicine cup. PREVYMIS oral pellets will not dissolve but will become loose or broken up. The entire mixture should be administered (see steps 3 and 4) within 2 hours.
3. Stir the mixture with the syringe and administer entire mixture right away using the syringe and NG tube or G tube.
4. Add room temperature water (see Rinse Volume in Table 4 and Table 5) to the medicine cup for rinsing, stir with a syringe and administer the entire rinse mixture using the syringe and NG tube or G tube.
5. Flush the NG tube or G tube with the volume of water recommended by the NG or G tube manufacturer.

Table 4: Recommendations for Administration of PREVYMIS Oral Pellets Via NG Tube
Dosage | NG Tube [Fr = French; PUR = polyurethane] | Syringe Type [With ENFit syringe, a medicine straw (large bore) is needed to aid withdrawal of the mixture from the medicine cup.] | Mixing Container | Initial Volume (mL) | Rinse Volume (mL)
120 mg to 480 mg | Any ≥ 8 Fr NG tube | Appropriately sized ENFit or catheter-tipped syringe | Medicine Cup | 15 | 15
40 mg to 80 mg | 5 Fr PUR NG tube or Any ≥ 6 Fr NG tube | Appropriately sized ENFit or catheter-tipped syringe | Medicine Cup | 3 | 2

Table 5: Recommendations for Administration of PREVYMIS Oral Pellets Via G Tube
Dosage | G Tube [Fr = French; PUR = polyurethane] | Syringe Type [With ENFit syringe, a medicine straw (large bore) is needed to aid withdrawal of the mixture from the medicine cup.] | Mixing Container | Initial Volume (mL) | Rinse Volume (mL)
120 mg to 480 mg | Any G tube | Appropriately sized ENFit or catheter-tipped syringe | Medicine Cup | 15 | 15
40 mg to 80 mg | Any 12 Fr G tube | Appropriately sized ENFit or catheter-tipped syringe | Medicine Cup | 3 | 2

2.10 Preparation and Administration of Intravenous Solution

PREVYMIS injection is supplied in 30 mL single-dose vials containing either 240 mg/12 mL per vial (20 mg/mL) or 480 mg/24 mL per vial (20 mg/mL).

PREVYMIS vials are for single use only. Discard any unused portion.

Preparation Instructions

- PREVYMIS must be diluted prior to intravenous (IV) use. Only 0.9% Sodium Chloride and 5% Dextrose are chemically and physically compatible with PREVYMIS injection.
- Do not shake PREVYMIS vial.
- Inspect vial contents for discoloration and particulate matter prior to dilution. PREVYMIS injection is a clear colorless solution and may contain a few product-related small translucent or white particles.
- Do not use the vial if the solution is cloudy, discolored, or contains matter other than a few small translucent or white particles.
- Once diluted, the solution of PREVYMIS is clear, and ranges from colorless to yellow. Variations of color within this range do not affect the quality of the product.
- Do not use PREVYMIS injection with IV bags and infusion set materials containing the plasticizer diethylhexyl phthalate (DEHP). Use only with IV bags and infusion set materials that are DEHP-free. Materials that are phthalate-free are also DEHP-free.
- Use compatible IV bags and infusion set materials. PREVYMIS injection is compatible with the following IV bags and infusion set materials. PREVYMIS injection is not recommended with any IV bags or infusion set materials not listed below (note that PREVYMIS injection is not recommended for use with polyurethane-containing IV administration set tubing).
  - IV Bags Materials:
    Polyvinyl chloride (PVC), ethylene vinyl acetate (EVA) and polyolefin (polypropylene and polyethylene)
  - Infusion Sets Materials:
    PVC, polyethylene (PE), polybutadiene (PBD), silicone rubber (SR), styrene–butadiene copolymer (SBC), styrene-butadiene-styrene copolymer (SBS), polystyrene (PS)
  - Plasticizers:
    Tris (2-ethylhexyl) trimellitate (TOTM), benzyl butyl phthalate (BBP)
  - Catheters:
    Radiopaque polyurethane
- For the 480 mg or 240 mg dose, add PREVYMIS injection (see Table 6) into a 250 mL pre-filled IV bag containing either 0.9% Sodium Chloride Injection, USP or 5% Dextrose Injection, USP and mix bag gently. Do not shake.
- For the 120 mg or 60 mg dose, add PREVYMIS injection into a pre-filled IV bag containing either 0.9% Sodium Chloride Injection, USP or 5% Dextrose Injection, USP (see Table 6) and mix bag gently. Do not shake.

Table 6: Preparation of PREVYMIS Intravenous Solution for Doses of 60 mg or Greater
PREVYMIS Dose | Volume of PREVYMIS 20 mg/mL to be Withdrawn from Vial | Volume of Diluent
480 mg | 24 mL | 250 mL
240 mg | 12 mL | 250 mL
120 mg | 6 mL | 100 mL
60 mg | 3 mL | 50 mL

- For the 40 mg dose, prepare a dilution of PREVYMIS injection according to Table 7 in either 0.9% Sodium Chloride Injection, USP or 5% Dextrose Injection, USP and mix bag gently. Transfer 20 mL from the prepared dilution into an appropriately sized IV bag or syringe. Do not shake.

Table 7: Preparation of PREVYMIS Intravenous Solution for Doses of 40 mg
PREVYMIS Dose | Preparation of 2 mg/mL PREVYMIS Dilution | Final Infusion Volume of the Prepared 2 mg/mL PREVYMIS Dilution
40 mg | Add 5 mL of 20 mg/mL PREVYMIS to 45 mL of diluent (0.9% Sodium Chloride Injection or 5% Dextrose Injection) and mix gently | 20 mL

Administration Instructions

- Administer the entire contents of the intravenous bag or syringe by intravenous infusion via a peripheral catheter or central venous line at a constant rate over 1 hour [see Dosage and Administration (2.1)].
- The diluted solution must be administered through a sterile 0.2 micron or 0.22 micron polyethersulfone (PES) in-line filter. Do not administer through a filter other than a sterile 0.2 micron or 0.22 micron PES in-line filter.
- Parenteral drug products should be inspected visually for particulate matter and discoloration prior to administration.
- Discard if the diluted solution is cloudy, discolored, or contains matter other than a few small translucent or white particles.

2.11 Storage of the Diluted Solution

The diluted solutions (as prepared in Table 6 or Table 7) are stable for up to 24 hours at room temperature or up to 48 hours under refrigeration at 2°C to 8°C (36°F to 46°F) (this time includes storage of the diluted solution in the intravenous bag through the duration of infusion).

2.12 Compatible Drug Products Used for Intravenous Administration

Compatible Drug Products

The physical compatibility of PREVYMIS injection with selected injectable drug products was evaluated in two commonly available diluents. PREVYMIS should not be co-administered through the same intravenous line (or cannula) with other drug products and diluent combinations except those listed below. Refer to the respective prescribing information of the co-administered drug(s) to confirm compatibility of simultaneous co-administration.

List of Compatible Drug Products when PREVYMIS and Drug Products are Prepared in 0.9% Sodium Chloride Injection, USP:

Ampicillin sodium, ampicillin sodium/sulbactam sodium, anti-thymocyte globulin, caspofungin, daptomycin, fentanyl citrate, fluconazole, furosemide, human insulin, magnesium sulfate, methotrexate, micafungin.

List of Compatible Drug Products when PREVYMIS and Drug Products are Prepared in 5% Dextrose Injection, USP:

Amphotericin B (lipid complex) [Amphotericin B (lipid complex) is compatible with PREVYMIS. However, Amphotericin B (liposomal) is incompatible [see Dosage and Administration (2.13)].] , anidulafungin, cefazolin sodium, ceftaroline, ceftriaxone sodium, doripenem, famotidine, folic acid, ganciclovir sodium, hydrocortisone sodium succinate, morphine sulfate, norepinephrine bitartrate, pantoprazole sodium, potassium chloride, potassium phosphate, tacrolimus, telavancin, tigecycline.

2.13 Incompatible Drug Products and Other Materials Used for Intravenous Administration

Incompatible Drug Products

PREVYMIS injection is physically incompatible with amiodarone hydrochloride, amphotericin B (liposomal), aztreonam, cefepime hydrochloride, ciprofloxacin, cyclosporine, diltiazem hydrochloride, filgrastim, gentamicin sulfate, levofloxacin, linezolid, lorazepam, midazolam HCl, mycophenolate mofetil hydrochloride, ondansetron, palonosetron.

Incompatible IV Bags and Infusion Set Materials

PREVYMIS injection is incompatible with diethylhexyl phthalate (DEHP) plasticizers and polyurethane-containing IV administration set tubing.

3 DOSAGE FORMS AND STRENGTHS

Tablets

- PREVYMIS 240 mg tablet: yellow oval tablet with "591" on one side and corporate logo on the other side.
- PREVYMIS 480 mg tablet: pink oval, bi-convex tablet with "595" on one side and corporate logo on the other side.

Oral Pellets

- PREVYMIS oral pellets: beige round pellets in packets. Each packet contains 20 mg letermovir.
- PREVYMIS oral pellets: beige round pellets in packets. Each packet contains 120 mg letermovir.

Injection

- PREVYMIS 240 mg/12 mL (20 mg/mL) injection: clear and colorless solution in a single-dose vial.
- PREVYMIS 480 mg/24 mL (20 mg/mL) injection: clear and colorless solution in a single-dose vial.

4 CONTRAINDICATIONS

- PREVYMIS is contraindicated in patients receiving pimozide or ergot alkaloids:
  - Pimozide: Concomitant administration of PREVYMIS in patients receiving pimozide may result in increased concentrations of pimozide due to inhibition of cytochrome P450 3A (CYP3A) by letermovir, which may lead to QT prolongation and torsades de pointes [see Warnings and Precautions (5.1) and Drug Interactions (7.2, 7.3)].
  - Ergot alkaloids: Concomitant administration of PREVYMIS in patients receiving ergot alkaloids may result in increased concentrations of ergot alkaloids (ergotamine and dihydroergotamine) due to inhibition of CYP3A by letermovir, which may lead to ergotism [see Warnings and Precautions (5.1) and Drug Interactions (7.2, 7.3)].
- PREVYMIS is contraindicated with pitavastatin and simvastatin when co-administered with cyclosporine. Concomitant administration of PREVYMIS in combination with cyclosporine may result in significantly increased pitavastatin or simvastatin concentrations, which may lead to myopathy or rhabdomyolysis [see Warnings and Precautions (5.1) and Drug Interactions (7.2, 7.3)].

5 WARNINGS AND PRECAUTIONS

5.1 Risk of Adverse Reactions or Reduced Therapeutic Effect Due to Drug Interactions

The concomitant use of PREVYMIS and certain drugs may result in potentially significant drug interactions, some of which may lead to adverse reactions (PREVYMIS or concomitant drugs) or reduced therapeutic effect of PREVYMIS or the concomitant drug [see Contraindications (4) and Drug Interactions (7.1, 7.2, 7.3)].

See Table 11 for steps to prevent or manage these possible or known significant drug interactions, including dosing recommendations. Consider the potential for drug interactions prior to and during PREVYMIS therapy; review concomitant medications during PREVYMIS therapy; and monitor for adverse reactions associated with PREVYMIS and concomitant medications.

5.2 Risks Associated with Hydroxypropyl Betadex Excipient in Intravenous Formulation

Intravenous formulation of PREVYMIS contains the excipient hydroxypropyl betadex. PREVYMIS injection should be used only in patients unable to take oral therapy and patients should be switched to oral PREVYMIS as soon as they are able to take oral medications. If possible, intravenous administration should not exceed 4 weeks [see Dosage and Administration (2.1)].

In patients with renal impairment, accumulation of hydroxypropyl betadex may occur. In adult patients with CLcr less than 50 mL/min and in pediatric patients with a similar degree of renal impairment (based on age-appropriate assessment of renal function) receiving PREVYMIS injection, closely monitor serum creatinine levels [see Dosage and Administration (2.7) and Use in Specific Populations (8.6)].

Animal studies have shown the potential for hydroxypropyl betadex to cause ototoxicity [see Nonclinical Toxicology (13.2)]. The active ingredient, letermovir, is not known to be associated with ototoxicity.

6 ADVERSE REACTIONS

6.1 Clinical Trials Experience

Because clinical trials are conducted under widely varying conditions, adverse reaction rates observed in the clinical trials of a drug cannot be directly compared to rates in the clinical trials of another drug and may not reflect the rates observed in practice.

Adult CMV-seropositive Recipients [R+] of an Allogeneic HSCT

Prophylaxis Through Week 14 (~100 days) Post-HSCT

The safety of PREVYMIS was evaluated in a Phase 3 randomized, double-blind, placebo-controlled trial (P001) in which 565 subjects were randomized and treated with PREVYMIS (N=373) or placebo (N=192) through Week 14 post-HSCT. Adverse events were those reported while subjects were on study medication or within two weeks of study medication completion/discontinuation. The mean time for reporting adverse events and laboratory abnormalities was approximately 22% longer in the PREVYMIS arm compared to the placebo arm.

Cardiac Adverse Events

The cardiac adverse event rate was higher in subjects receiving PREVYMIS (13%) compared to subjects receiving placebo (6%). The most common cardiac adverse events were tachycardia (reported in 4% of PREVYMIS subjects and in 2% of placebo subjects) and atrial fibrillation (reported in 3% of PREVYMIS subjects and in 1% of placebo subjects). Among those subjects who experienced one or more cardiac adverse events, 85% of PREVYMIS and 92% of placebo subjects had events reported as mild or moderate in severity.

Common Adverse Events

The rate of adverse events occurring in at least 10% of subjects in the PREVYMIS group and at a frequency at least 2% greater than placebo are outlined in Table 8.

Table 8: Trial P001 All Grade Adverse Events Reported in ≥ 10% of PREVYMIS-Treated HSCT Recipients at a Frequency at least 2% Greater than Placebo
Adverse Events | PREVYMIS (N=373) | Placebo (N=192)
nausea | 27% | 23%
diarrhea | 26% | 24%
vomiting | 19% | 14%
peripheral edema | 14% | 9%
cough | 14% | 10%
headache | 14% | 9%
fatigue | 13% | 11%
abdominal pain | 12% | 9%

Overall, similar proportions of subjects in each group discontinued study medication due to an adverse event (13% of PREVYMIS subjects vs. 12% of placebo subjects). The most frequently reported adverse event that led to study drug discontinuation was nausea, occurring in 2% of PREVYMIS subjects and 1% of placebo subjects. Hypersensitivity reaction, with associated moderate dyspnea, occurred in one subject following the first infusion of IV PREVYMIS after switching from oral PREVYMIS, leading to treatment discontinuation.

Laboratory Abnormalities

Selected laboratory abnormalities reported during treatment or within 2 weeks of stopping treatment are presented in Table 9.

Table 9: Trial P001 Selected Laboratory Abnormalities
 | PREVYMIS N=373 | Placebo N=192
Absolute neutrophil count (cells/μL)
< 500 | 19% | 19%
500 – < 750 | 4% | 7%
750 – < 1000 | 8% | 9%
Hemoglobin (g/dL)
< 6.5 | 2% | 1%
6.5 – < 8.0 | 14% | 15%
8.0 – < 9.5 | 41% | 43%
Platelets (cells/μL)
< 25000 | 27% | 21%
25000 – < 50000 | 17% | 18%
50000 – < 100000 | 20% | 30%
Serum creatinine (mg/dL)
> 2.5 | 2% | 3%
> 1.5 – 2.5 | 17% | 20%

The median time to engraftment (defined as absolute neutrophil count ≥ 500/mm^3 on 3 consecutive days after transplantation) was 19 days in the PREVYMIS group and 18 days in the placebo group.

Prophylaxis From Week 14 (~100 days) Through Week 28 (~200 days) Post-HSCT

The safety of PREVYMIS was evaluated in a Phase 3 randomized, double-blind, placebo-controlled trial (P040) in which 218 subjects who completed PREVYMIS prophylaxis through ~100 days post-HSCT were randomized to treatment with PREVYMIS (N=144) or placebo (N=74) through Week 28 (~200 days) post-HSCT. Adverse events were those reported while subjects were on study drug or within two weeks of study drug completion/discontinuation.

The most commonly reported adverse events in P040 were similar to those reported in P001. Study drug was discontinued due to an adverse event in 5% of PREVYMIS subjects and 1% of placebo subjects. The cardiac adverse event rate was 4% in the PREVYMIS and placebo groups.

The rates of hematologic laboratory abnormalities were comparable in the PREVYMIS and placebo groups. Serum creatinine abnormalities > 1.5 mg/dL occurred in 15% of PREVYMIS and 8% of placebo subjects.

Adult Kidney Transplant Recipients [D+/R-]

The safety of PREVYMIS was evaluated in a Phase 3 randomized, double-blind, active comparator-controlled trial (P002) in which 589 subjects were treated with PREVYMIS (N=292) or valganciclovir (N=297) through Week 28 post-transplant. Adverse events were those reported while subjects were on study medication or within two weeks of study medication completion/discontinuation. In these subjects, diarrhea was reported in at least 10% of subjects in the PREVYMIS group and at a frequency greater than valganciclovir (PREVYMIS, 32%; valganciclovir, 29%). Study drug was discontinued due to an adverse event in 4% of PREVYMIS subjects and 14% of valganciclovir subjects. The most frequently reported adverse events that led to study drug discontinuation were neutropenia (PREVYMIS, 1%; valganciclovir, 2%) and leukopenia (PREVYMIS, 1%; valganciclovir, 5%).

Laboratory Abnormalities

Selected laboratory abnormalities reported through Week 28 post-transplant are presented in Table 10.

Table 10: Trial P002 Selected Laboratory Abnormalities
 | PREVYMIS N=292 | Valganciclovir N=297
Absolute neutrophil count (cells/μL)
< 500 | 2% | 7%
500 – < 750 | 1% | 4%
750 – < 1000 | 1% | 8%
Total < 1000 | 5% | 18%
Hemoglobin (g/dL)
< 6.5 | 2% | 0%
6.5 – < 8.0 | 4% | 5%
8.0 – < 9.5 | 29% | 32%
Total < 9.5 | 34% | 37%
Platelets (cells/μL)
< 50000 | 0% | 0%
50000 – < 100000 | 1% | 3%
Total < 100000 | 1% | 3%
Leukocytes (cells/μL)
< 1000 | 1% | 2%
1000 – < 2000 | 5% | 19%
2000 – < 2500 | 4% | 14%
Total < 2500 | 10% | 35%
Serum creatinine (mg/dL)
> 2.5 | 24% | 22%
> 1.5 – 2.5 | 49% | 52%
Total > 1.5 | 73% | 73%

Pediatric Recipients of an Allogeneic HSCT

The safety of PREVYMIS was evaluated in 63 pediatric subjects aged 2 months to less than 18 years of age who received an allogeneic HSCT (P030). PREVYMIS was administered orally (tablet or pellet) or intravenously. The duration of PREVYMIS exposure ranged from 3 days to 102 days (median duration 84 days). The safety profile was consistent with the safety profile observed in clinical trials of PREVYMIS in adults [see Use in Specific Populations (8.4) and Clinical Studies (14.4)].

7 DRUG INTERACTIONS

7.1 Potential for Other Drugs to Affect PREVYMIS

Letermovir is a substrate of organic anion-transporting polypeptide 1B1/3 (OATP1B1/3) and P-glycoprotein (P-gp) transporters and UDP-glucuronosyltransferase 1A1/3 (UGT1A1/3) enzymes. Co-administration of PREVYMIS with drugs that are inhibitors of OATP1B1/3 transporters may result in increases in letermovir plasma concentrations (Table 11).

Co-administration of PREVYMIS with inducers of transporters (e.g., P-gp) and/or enzymes (e.g., UGTs) is not recommended due to the potential for a decrease in letermovir plasma concentrations (see Table 11).

7.2 Potential for PREVYMIS to Affect Other Drugs

Co-administration of PREVYMIS with midazolam results in increased midazolam plasma concentrations, indicating that letermovir is a moderate inhibitor of CYP3A [see Clinical Pharmacology (12.3)]. Co-administration of PREVYMIS with drugs that are CYP3A substrates may result in clinically relevant increases in the plasma concentrations of co-administered CYP3A substrates (Table 11) [see Contraindications (4) and Warnings and Precautions (5.1)].

Letermovir is an inhibitor of OATP1B1/3 transporters. Co-administration of PREVYMIS with drugs that are substrates of OATP1B1/3 transporters may result in a clinically relevant increase in plasma concentrations of co-administered OATP1B1/3 substrates (Table 11).

The magnitude of CYP3A- and OATP1B1/3-mediated drug interactions on co-administered drugs may be different when PREVYMIS is co-administered with cyclosporine. See the prescribing information for cyclosporine for information on drug interactions with cyclosporine.

7.3 Established and Other Potentially Significant Drug Interactions

If dose adjustments of concomitant medications are made due to treatment with PREVYMIS, doses should be readjusted after treatment with PREVYMIS is completed.

Table 11 provides a listing of established or potentially clinically significant drug interactions. The drug interactions described are based on adult studies conducted with PREVYMIS or are predicted drug interactions that may occur with PREVYMIS [see Contraindications (4), Warnings and Precautions (5.1), and Clinical Pharmacology (12.3)].

Table 11: Potentially Significant Drug Interactions: Alteration in Dose May Be Recommended Based on Results from Adult Drug Interaction Studies or Predicted Interactions [This table is not all inclusive.] (Information in the Table Applies to Co-administration of PREVYMIS and the Concomitant Drug without Cyclosporine, Unless Otherwise Indicated)
Concomitant Drug Class and/or Clearance Pathway: Drug Name | Effect on Concentration [↓ =decrease, ↑ =increase] | Clinical Comments
Anti-arrhythmic Agents
amiodarone | ↑ amiodarone | Close clinical monitoring for adverse events related to amiodarone is recommended during co-administration. Frequently monitor amiodarone concentrations when amiodarone is co-administered with PREVYMIS.
Antibiotics
nafcillin | ↓ letermovir | Co-administration of PREVYMIS and nafcillin is not recommended due to potential for loss of efficacy of PREVYMIS.
Anticoagulants
warfarin | ↓ warfarin | When PREVYMIS is co-administered with warfarin, frequently monitor International Normalized Ratio (INR) [Refer to the respective prescribing information.] .
Anticonvulsants
carbamazepine | ↓ letermovir | Co-administration of PREVYMIS and carbamazepine is not recommended due to potential for loss of efficacy of PREVYMIS.
phenobarbital | ↓ letermovir | Co-administration of PREVYMIS and phenobarbital is not recommended due to potential for loss of efficacy of PREVYMIS.
phenytoin | ↓ letermovir ↓ phenytoin | Co-administration of PREVYMIS and phenytoin is not recommended due to potential for loss of efficacy of PREVYMIS.
Antidiabetic Agents
Examples: glyburide, repaglinide, rosiglitazone | ↑ glyburide ↑ repaglinide ↑ rosiglitazone | When PREVYMIS is co-administered with glyburide, repaglinide, or rosiglitazone, frequently monitor glucose concentrations. When PREVYMIS is co-administered with cyclosporine, use of repaglinide is not recommended.
Antifungals
voriconazole [These interactions have been studied [see Clinical Pharmacology (12.3)].] | ↓ voriconazole | If concomitant administration of voriconazole is necessary, closely monitor for reduced effectiveness of voriconazole.
Antimycobacterials
rifabutin | ↓ letermovir | Co-administration of PREVYMIS and rifabutin is not recommended due to potential for loss of efficacy of PREVYMIS.
rifampin | ↓ letermovir | Co-administration of PREVYMIS and rifampin is not recommended due to potential for loss of efficacy of PREVYMIS.
Antipsychotics
pimozide | ↑ pimozide | Co-administration is contraindicated due to risk of QT prolongation and torsades de pointes [see Contraindications (4)].
thioridazine | ↓ letermovir | Co-administration of PREVYMIS and thioridazine is not recommended due to potential for loss of efficacy of PREVYMIS.
Endothelin Antagonists
bosentan | ↓ letermovir | Co-administration of PREVYMIS and bosentan is not recommended due to potential for loss of efficacy of PREVYMIS.
Ergot Alkaloids
ergotamine, dihydroergotamine | ↑ ergotamine, dihydroergotamine | Co-administration is contraindicated due to risk of ergotism [see Contraindications (4)].
Herbal Products
St. John's wort (Hypericum perforatum) | ↓ letermovir | Co-administration of PREVYMIS and St. John's wort is not recommended due to potential for loss of efficacy of PREVYMIS.
HIV Medications
efavirenz | ↓ letermovir | Co-administration of PREVYMIS and efavirenz is not recommended due to potential for loss of efficacy of PREVYMIS.
etravirine | ↓ letermovir | Co-administration of PREVYMIS and etravirine is not recommended due to potential for loss of efficacy of PREVYMIS.
nevirapine | ↓ letermovir | Co-administration of PREVYMIS and nevirapine is not recommended due to potential for loss of efficacy of PREVYMIS.
HMG-CoA Reductase Inhibitors
atorvastatin | ↑ atorvastatin | When PREVYMIS is co-administered with atorvastatin, do not exceed an atorvastatin dosage of 20 mg daily. Closely monitor patients for myopathy and rhabdomyolysis. When PREVYMIS is co-administered with cyclosporine, use of atorvastatin is not recommended.
pitavastatin, simvastatin | ↑ HMG-CoA reductase inhibitors | Co-administration of PREVYMIS and pitavastatin or simvastatin is not recommended. When PREVYMIS is co-administered with cyclosporine, use of either pitavastatin or simvastatin is contraindicated due to significantly increased pitavastatin or simvastatin concentrations and risk of myopathy or rhabdomyolysis [see Contraindications (4)].
fluvastatin, lovastatin, pravastatin, rosuvastatin | ↑ HMG-CoA reductase inhibitors | When PREVYMIS is co-administered with these statins, a statin dosage reduction may be necessary. Closely monitor patients for myopathy and rhabdomyolysis. When PREVYMIS is co-administered with cyclosporine, use of lovastatin is not recommended. When PREVYMIS is co-administered with cyclosporine, refer to the statin prescribing information for specific statin dosing recommendations.
Immunosuppressants
cyclosporine | ↑ cyclosporine ↑ letermovir | Decrease the dosage of PREVYMIS to 240 mg once daily in adult and pediatric patients 12 years of age and older [see Dosage and Administration (2.4) and Clinical Pharmacology (12.3)]. Dose adjustment may be required in pediatric patients less than 12 years of age [see Dosage and Administration (2.6) and Clinical Pharmacology (12.3)]. Frequently monitor cyclosporine whole blood concentrations during treatment and after discontinuation of PREVYMIS and adjust the dose of cyclosporine accordingly.
sirolimus | ↑ sirolimus | When PREVYMIS is co-administered with sirolimus, frequently monitor sirolimus whole blood concentrations during treatment and after discontinuation of PREVYMIS and adjust the dose of sirolimus accordingly. When PREVYMIS is co-administered with cyclosporine and sirolimus, refer to the sirolimus prescribing information for specific sirolimus dosing recommendations.
tacrolimus | ↑ tacrolimus | Frequently monitor tacrolimus whole blood concentrations during treatment and after discontinuation of PREVYMIS and adjust the dose of tacrolimus accordingly.
Proton Pump Inhibitors
omeprazole | ↓ omeprazole | Clinical monitoring and dose adjustment may be needed.
pantoprazole | ↓ pantoprazole | Clinical monitoring and dose adjustment may be needed.
Wakefulness-Promoting Agents
modafinil | ↓ letermovir | Co-administration of PREVYMIS and modafinil is not recommended due to potential for loss of efficacy of PREVYMIS.
CYP3A Substrates
Examples: alfentanil, fentanyl, midazolam, and quinidine | ↑ CYP3A substrate | When PREVYMIS is co-administered with a CYP3A substrate, refer to the prescribing information for dosing of the CYP3A substrate with a moderate CYP3A inhibitor. When PREVYMIS is co-administered with cyclosporine, the combined effect on CYP3A substrates may be similar to a strong CYP3A inhibitor. Refer to the prescribing information for dosing of the CYP3A substrate with a strong CYP3A inhibitor. CYP3A substrates pimozide and ergot alkaloids are contraindicated [see Contraindications (4)].

7.4 Drugs without Clinically Significant Interactions with PREVYMIS

No clinically significant interactions were observed in adult clinical drug-drug interaction studies of letermovir and acyclovir, digoxin, mycophenolate mofetil, fluconazole, itraconazole, posaconazole, ethinyl estradiol, and levonorgestrel.

8 USE IN SPECIFIC POPULATIONS

8.1 Pregnancy

Risk Summary

No adequate human data are available to establish whether PREVYMIS poses a risk to pregnancy outcomes. In animal reproduction studies, embryo-fetal developmental toxicity (including fetal malformations) was observed in rats during the period of organogenesis at letermovir exposures (AUC) 11 times higher than human exposure at the recommended human dose (RHD). In rabbits, no embryo-fetal developmental toxicity was noted at exposures that were not maternally toxic (up to letermovir exposures 2 times higher than human exposure at the RHD). In a rat pre/post-natal development study, total litter loss was observed at maternal letermovir exposures approximately 2 times higher than human exposure at the RHD (see Data).

The background risk of major birth defects and miscarriage for the indicated population is unknown. In the U.S. general population, the estimated background risk of major birth defects and miscarriage in clinically recognized pregnancies is 2-4% and 15-20%, respectively.

Data

Animal Data

Letermovir was administered orally to pregnant rats at 0, 10, 50 or 250 mg/kg/day from gestation days 6 to 17. Developmental toxicities, including skeletal malformations and umbilical cord shortening, were observed at 250 mg/kg/day (approximately 11 times higher than human exposure at the RHD). In addition, decreased fetal body weight and skeletal variations (due to maternal toxicity) were observed at this dose. No embryo-fetal toxicities were observed at 50 mg/kg/day (approximately 3 times higher than human exposure at the RHD).

Letermovir was administered orally to pregnant rabbits at 0, 25, 75 or 225 mg/kg/day from gestation days 6 to 20. Developmental toxicities, including spontaneous abortion, increased post-implantation loss, and skeletal variations, were observed at a maternally toxic dose (225 mg/kg/day; approximately 2 times higher than human exposure at the RHD). No embryo-fetal toxicities were observed at 75 mg/kg/day (less than human exposure at the RHD).

In the pre/post-natal development study, letermovir was administered orally to pregnant rats at 0, 10, 45 or 180 mg/kg/day from gestation day 6 to lactation day 22. At 180 mg/kg/day (approximately 2 times higher than human exposure at the RHD), total litter loss due to stillbirth or possible maternal neglect was observed in 5 of 23 pregnant females by post-partum/lactation day 4. In surviving offspring, slight developmental delays in vaginal opening and pinna unfolding were accompanied by reduced body weight gain at this dose. No toxicities were observed at 45 mg/kg/day (similar to human exposure at the RHD).

8.2 Lactation

Risk Summary

It is not known whether letermovir is present in human breast milk, affects human milk production, or has effects on the breastfed child.

When administered to lactating rats, letermovir was present in the milk of lactating rats as well as the blood of nursing pups (see Data).

The developmental and health benefits of breastfeeding should be considered along with the mother's clinical need for PREVYMIS and any potential adverse effects on the breastfed child from PREVYMIS or from the underlying maternal condition.

Data

In a lactation study, letermovir was excreted in milk when administered intravenously (at 10 mg/kg) to lactating rats on post-partum/lactation day 10. Letermovir was also detected in the blood of nursing pups on post-partum/lactation day 21 in the pre/post-natal developmental study.

8.3 Females and Males of Reproductive Potential

Infertility

There are no data on the effect of letermovir on human fertility. Decreased fertility due to testicular toxicity was observed in male rats [see Nonclinical Toxicology (13.1, 13.2)].

8.4 Pediatric Use

The safety and effectiveness of PREVYMIS have been established for:

- Prophylaxis of CMV infection and disease in pediatric CMV-seropositive recipients of an allogeneic HSCT 6 months of age and older and weighing at least 6 kg, and
- Prophylaxis of CMV disease in pediatric kidney transplant recipients 12 years of age and older and weighing at least 40 kg who are at high risk [D+/R-].

HSCT Recipients: The use of PREVYMIS for prophylaxis of CMV infection and disease in pediatric recipients of an allogeneic HSCT is supported by evidence from adequate and well-controlled studies in adults with additional pharmacokinetic and safety data from pediatric patients in Trial P030. The safety and pharmacokinetic results were similar to those in adults [see Warnings and Precautions (5.2), Adverse Reactions (6.1), Clinical Pharmacology (12.3), Clinical studies (14.2, 14.4)].

Kidney Transplant Recipients: The use of PREVYMIS for prophylaxis of CMV disease in high-risk [D+/R-] kidney transplant recipients 12 years of age and older and weighing at least 40 kg is supported by evidence from an adequate and well-controlled study in adults and safety data from pediatric HSCT recipients (Trial P030). Letermovir exposures are expected to be similar between adult and pediatric patients 12 years of age and older and weighing at least 40 kg [see Warnings and Precautions (5.2), Adverse Reactions (6.1), Clinical Pharmacology (12.3), Clinical studies (14.3, 14.4)].

The safety and effectiveness of PREVYMIS have not been established for:

- HSCT recipients less than 6 months of age or weighing less than 6 kg, or
- Kidney transplant recipients less than 12 years of age or weighing less than 40 kg.

8.5 Geriatric Use

Of the 373 subjects treated with PREVYMIS in Trial P001, 56 (15%) subjects were 65 years of age or older. Of the 144 subjects treated with PREVYMIS in Trial P040, 32 (22%) subjects were 65 years of age or older. Of the 292 subjects treated with PREVYMIS in Trial P002, 48 (16%) subjects were 65 years of age or older. Safety and efficacy were similar across older and younger subjects in each trial. No dosage adjustment of PREVYMIS is required based on age [see Clinical Pharmacology (12.3)].

8.6 Renal Impairment

For adult patients with CLcr greater than 10 mL/min (by Cockcroft-Gault equation), and pediatric patients with a similar degree of renal impairment (based on age-appropriate assessment of renal function), no dosage adjustment of PREVYMIS is required based on renal impairment [see Clinical Pharmacology (12.3)]. The safety of PREVYMIS in adult patients with end-stage renal disease (CLcr less than 10 mL/min) or in pediatric patients with a similar degree of renal impairment (based on age-appropriate assessment of renal function), including patients on dialysis, is unknown.

In adult patients with CLcr less than 50 mL/min and in pediatric patients with a similar degree of renal impairment (based on age-appropriate assessment of renal function) receiving PREVYMIS injection, accumulation of the intravenous vehicle, hydroxypropyl betadex, could occur. Closely monitor serum creatinine levels in these patients [see Dosage and Administration (2.7) and Warnings and Precautions (5.2)].

8.7 Hepatic Impairment

No dosage adjustment of PREVYMIS is required for patients with mild (Child-Pugh Class A) or moderate (Child-Pugh Class B) hepatic impairment. PREVYMIS is not recommended for patients with severe (Child-Pugh Class C) hepatic impairment [see Clinical Pharmacology (12.3)].

10 OVERDOSAGE

There is no specific antidote for overdose with PREVYMIS. In case of overdose, it is recommended that the patient be monitored for adverse reactions and appropriate symptomatic treatment be instituted.

It is unknown whether dialysis will result in meaningful removal of PREVYMIS from systemic circulation.

11 DESCRIPTION

PREVYMIS contains letermovir, an inhibitor of the CMV DNA terminase complex, and is administered orally or by intravenous infusion.

Letermovir has a molecular formula of C29H28F4N4O4 and a molecular weight of 572.55. The chemical name for letermovir is (4S)-2-{8-Fluoro-2-[4-(3- methoxyphenyl)piperazin-1-yl]-3-[2-methoxy-5- (trifluoromethyl)phenyl]-3,4-dihydroquinazolin-4-yl}acetic acid. Letermovir is very slightly soluble in water.

The chemical structure of letermovir is:

PREVYMIS is available as 240 mg and 480 mg tablets. PREVYMIS tablets contain either 240 mg or 480 mg of letermovir and the following inactive ingredients: colloidal silicon dioxide, croscarmellose sodium, magnesium stearate, microcrystalline cellulose, povidone 25, and film-coated with a coating material containing the following inactive ingredients: hypromellose 2910, iron oxide red (only for 480 mg tablets), iron oxide yellow, lactose monohydrate, titanium dioxide, and triacetin. Carnauba wax is added as a polishing agent.

PREVYMIS is available as 20 mg and 120 mg packets of oral pellets. PREVYMIS packets of oral pellets contain either 20 mg or 120 mg of letermovir. PREVYMIS oral pellets contain the following inactive ingredients: colloidal silicon dioxide, croscarmellose sodium, magnesium stearate, microcrystalline cellulose, povidone K-29/32, and are film-coated with a coating material containing the following inactive ingredients: hypromellose 2910, iron oxide red, iron oxide yellow, lactose monohydrate, titanium dioxide, and triacetin.

PREVYMIS is also available as 240 mg/12 mL (20 mg/mL) and 480 mg/24 mL (20 mg/mL) injection for intravenous infusion. PREVYMIS injection is a clear, preservative-free sterile solution and may contain a few small translucent or white particles in single-dose vials of either 240 mg or 480 mg per vial. Each 1 mL of solution contains 20 mg letermovir, hydroxypropyl betadex (150 mg), sodium chloride (3.1 mg), sodium hydroxide (1.2 mg), and Water for Injection. The amount of sodium hydroxide may be adjusted to achieve a pH of approximately 7.5.

12 CLINICAL PHARMACOLOGY

12.1 Mechanism of Action

PREVYMIS is an antiviral drug against CMV [see Microbiology (12.4)].

12.2 Pharmacodynamics

Cardiac Electrophysiology

In a thorough QT trial in healthy adult subjects, letermovir at the therapeutic IV dose or at a dose of 2 times the approved IV dose did not prolong QTc to any clinically relevant extent.

12.3 Pharmacokinetics

The pharmacokinetic properties of letermovir are displayed in Table 12.

Table 12: Absorption, Distribution, Metabolism, Elimination (ADME), and Pharmacokinetic Properties of PREVYMIS [Values were obtained in studies of healthy adult subjects unless otherwise indicated.]
Pharmacokinetics in Adult HSCT Recipients
Treatment Regimen | Steady-state median (90% prediction interval) AUC (ng∙hr/mL) of PREVYMIS
480 mg oral once daily, no cyclosporine | 34,400 (16,900, 73,700)
480 mg IV once daily, no cyclosporine | 100,000 (65,300, 148,000)
240 mg oral once daily, with cyclosporine | 60,800 (28,700, 122,000)
240 mg IV once daily, with cyclosporine | 70,300 (46,200, 106,000)
Pharmacokinetics in Adult Kidney Transplant Recipients
Treatment Regimen | Steady-state median (90% prediction interval) AUC (ng∙hr/mL) of PREVYMIS
480 mg oral once daily, no cyclosporine | 62,700 (17,500, 139,000)
240 mg oral once daily, with cyclosporine | 71,900 (42,400, 125,000)
Pharmacokinetics in Adult Healthy Subjects
Treatment Regimen | Steady-state geometric mean AUC and Cmax of PREVYMIS
480 mg oral once daily | Cmax: 13,000 ng/mL
 | AUC: 71,500 ng•hr/mL
Dose proportionality | Greater than proportional following single and multiple oral or IV doses of PREVYMIS 240 mg and 480 mg
Accumulation ratio [Based on geometric mean data.] | Cmax: 1.03 AUC: 1.22
Time to steady-state | 9-10 days
Absorption
Bioavailability | Healthy adult subjects administered PREVYMIS without cyclosporine: 94% at an oral dose range of 240 mg to 480 mg Adult HSCT recipients administered PREVYMIS without cyclosporine: 35% with 480 mg oral once daily Adult HSCT recipients administered PREVYMIS with cyclosporine: 85% with 240 mg oral once daily Adult kidney transplant recipients administered PREVYMIS without cyclosporine: 56% [95% CI (46%, 65%)] with 480 mg oral once daily
Median Tmax (hr) | 1.5 to 3.0 hr
Effect of food (relative to fasting) [Values refer to geometric mean ratio [fed/fasted] percentage and 90% confidence interval back transformed from linear mixed-effects model performed on natural log-transformed values. The meal administered was a standard high fat and high calorie meal (33 grams protein, 65 grams carbohydrates, 58 grams fat; 920 total calories).] | AUC: 99.63% [84.27% - 117.80%] Cmax: 129.82% [104.35% -161.50%]
Oral pellets versus tablet (fasting) | AUC and Cmax values were comparable when comparing PREVYMIS tablet (240 mg) and PREVYMIS oral pellets (2 X 120 mg)
Distribution
Mean steady-state volume of distribution | 45.5 L following IV administration in adult HSCT recipients
% In vitro bound to human plasma proteins | 99% across the concentration range of 0.2 to 50 mg/L
In vitro blood-to plasma ratio | 0.56 across the concentration range of 0.1 to 10 mg/L
Metabolism
In vitro metabolism | UGT1A1/1A3 (minor)
Drug-related component in plasma | 97% unchanged parent No major metabolites detected in plasma
Elimination
Route of elimination | Hepatic uptake (OATP1B1/3)
Mean terminal t1/2 (hr) | 12 hrs after dosing of PREVYMIS 480 mg IV once daily
% of dose excreted in feces [Single oral administration of radiolabeled letermovir in mass balance study.] | 93%
% of dose excreted in urine | <2%
% of unchanged drug excreted in feces | 70%

Specific Populations

Pediatric Patients

Letermovir AUC in pediatric HSCT recipients was estimated using population pharmacokinetic analysis using Trial P030 data (see Table 13 and Table 14). Exposures for pediatric HSCT recipients for body weight bands 6 kg and above are within the range of exposures observed at the recommended doses of PREVYMIS in adults (see Table 12).

Table 13: PREVYMIS AUC (ng•hr/mL) Values Following Once Daily Oral Administration in Pediatric HSCT Recipients
Body Weight | Oral Dose, No Cyclosporine | Steady-state Median (90% Prediction Interval) [Medians and 90% prediction intervals are based on simulations using the pediatric HSCT population PK model with inter-individual variability.] | Oral Dose, With Cyclosporine | Steady-state Median (90% Prediction Interval)
30 kg and above [Includes pediatric patients 12 years of age and older or weighing ≥ 30 kg.] | 480 mg | 38,500 (18,100, 78,100) | 240 mg | 50,200 (24,100, 102,000)
15 kg to less than 30 kg | 240 mg | 39,600 (21,300, 71,800) | 120 mg | 53,200 (27,800, 102,000)
7.5 kg to less than 15 kg | 120 mg | 32,900 (16,800, 61,200) | 60 mg | 42,300 (22,300, 81,500)
6 kg to less than 7.5 kg [Includes pediatric patients 6 months of age and older and weighing 6 kg to < 7.5 kg.] | 80 mg | 29,400 (16,600, 54,100) | 40 mg | 39,200 (20,900, 71,800)

Table 14: PREVYMIS AUC (ng•hr/mL) Values Following Once Daily IV Administration in Pediatric HSCT Recipients
Body Weight | IV Dose, No Cyclosporine | Steady-state Median (90% Prediction Interval) [Medians and 90% prediction intervals are based on simulations using the pediatric HSCT population PK model with inter-individual variability.] | IV Dose, With Cyclosporine | Steady-state Median (90% Prediction Interval)
30 kg and above [Includes pediatric patients 12 years of age and older or weighing ≥ 30 kg.] | 480 mg | 114,000 (53,900, 230,000) | 240 mg | 61,400 (29,300, 128,000)
15 kg to less than 30 kg | 120 mg | 56,400 (29,100, 110,000) | 120 mg | 62,300 (32,100, 114,000)
7.5 kg to less than 15 kg | 60 mg | 45,900 (24,500, 86,400) | 60 mg | 49,900 (26,300, 96,300)
6 kg to less than 7.5 kg [Includes pediatric patients 6 months of age and older and weighing 6 kg to < 7.5 kg.] | 40 mg | 42,800 (23,800, 79,200) | 40 mg | 46,400 (26,300, 86,500)

Age, Gender, Race, and Weight

Age (18 to 82 years), gender, race, and body weight (up to 100 kg) did not have a clinically significant effect on the pharmacokinetics of letermovir in adult subjects.

Renal Impairment

Clinical Study in a Renally Impaired Population

Letermovir AUC was approximately 1.9- and 1.4-fold higher in adult subjects with moderate (eGFR greater than or equal to 30 to 59 mL/min/1.73m^2) and severe (eGFR less than 30 mL/min/1.73m^2) renal impairment, respectively, compared to healthy adult subjects.

Post-kidney Transplant

Based on population pharmacokinetic analysis, letermovir AUC was approximately 1.1-, 1.3- and 1.4-fold higher in adult subjects with mild (CLcr greater than or equal to 60 to less than 90 mL/min), moderate (CLcr greater than or equal to 30 to less than 60 mL/min) and severe (CLcr greater than or equal to 15 to less than 30 mL/min) renal impairment, respectively, compared to adult subjects with CLcr greater than or equal to 90 mL/min.

Intravenous Formulation

Hydroxypropyl betadex present in the intravenous letermovir formulation is mainly eliminated by glomerular filtration. Decreased elimination of hydroxypropyl betadex has been reported in the literature in patients with severe renal impairment.

Hepatic Impairment

Letermovir AUC was approximately 1.6- and 3.8-fold higher in adult subjects with moderate (Child-Pugh Class B [CP-B], score of 7-9) and severe (Child-Pugh Class C [CP-C], score of 10-15) hepatic impairment, respectively, compared to healthy adult subjects.

Drug Interaction Studies

Drug interaction studies were performed in healthy adult subjects with PREVYMIS and drugs likely to be co-administered or drugs commonly used as probes for pharmacokinetic interactions (see Table 15 and Table 16).

In vitro results indicate that letermovir is a substrate of drug metabolizing enzymes CYP3A, CYP2D6, UGT1A1, and UGT1A3, and transporters OATP1B1/3 and P-gp. Oxidative metabolism is considered to be a minor elimination pathway based on in vivo human data. Inhibitors of OATP1B1/3 may result in increases in letermovir plasma concentrations. Changes in letermovir plasma concentrations due to inhibition of P-gp/BCRP by itraconazole were not clinically relevant. Changes in letermovir plasma concentrations due to inhibition of UGTs are not anticipated to be clinically relevant.

Based on in vitro studies, the metabolism of letermovir is not mediated by CYP1A2, CYP2A6, CYP2B6, CYP2C8, CYP2C9, CYP2C18, CYP2C19, CYP2E1, CYP4A11, UGT1A4, UGT1A6, UGT1A7, UGT1A8, UGT1A9, UGT1A10, UGT2B4, UGT2B7, UGT2B15, or UGT2B17. The transport of letermovir is not mediated by OATP2B1, OCT1, OAT1, BCRP, or MRP2 in vitro.

Letermovir is a time-dependent inhibitor and inducer of CYP3A in vitro. Co-administration of PREVYMIS with midazolam resulted in increased exposure of midazolam, indicating that the net effect of letermovir on CYP3A is moderate inhibition (see Table 16). Based on these results, co-administration of PREVYMIS with CYP3A substrates may increase the plasma concentrations of the CYP3A substrates [see Contraindications (4), Warnings and Precautions (5.1), Drug Interactions (7.2, 7.3), and Table 11]. Letermovir is a reversible inhibitor of CYP2C8 in vitro. When co-administered with PREVYMIS, plasma concentrations of CYP2C8 substrates are predicted to be increased [see Table 11 in Drug Interactions (7.3)]. Co-administration of PREVYMIS reduced the exposure of voriconazole, most likely due to the induction of voriconazole elimination pathways, CYP2C9 and CYP2C19. Co-administration of PREVYMIS with CYP2C9 and CYP2C19 substrates may decrease the plasma concentrations of the CYP2C9 and CYP2C19 substrates [see Table 11 in Drug Interactions (7.3)]. Letermovir is an inducer of CYP2B6 in vitro; the clinical relevance is unknown.

Letermovir inhibited efflux transporters P-gp, breast cancer resistance protein (BCRP), bile salt export pump (BSEP), multidrug resistance-associated protein 2 (MRP2), OAT3, and hepatic uptake transporter OATP1B1/3 in vitro. Co-administration of PREVYMIS with substrates of OATP1B1/3 transporters (e.g., atorvastatin, a known substrate of CYP3A, OATP1B1/3, and potentially BCRP) may result in a clinically relevant increase in plasma concentrations of OATP1B1/3 substrates [see Table 11 in Drug Interactions (7.3)]. There were no clinically relevant changes in plasma concentrations of digoxin, a P-gp substrate, or acyclovir, an OAT3 substrate, following co-administration with PREVYMIS in clinical studies (see Table 16). The effect of letermovir on BCRP, BSEP, and MRP2 substrates was not evaluated in clinical studies; the clinical relevance is unknown.

Based on in vitro results letermovir is not an inhibitor of CYP1A2, CYP2A6, CYP2C9, CYP2C19, CYP2D6, CYP2E1, UGT1A4, UGT1A6, UGT1A9, or UGT2B7 and is not an inducer of CYP1A2. Letermovir is not an inhibitor of OATP2B1, OCT1, OCT2, or OAT1 in vitro.

Table 15: Drug Interactions: Changes in Pharmacokinetics of Letermovir in the Presence of Co-administered Drug
Co-administered Drug | Regimen of Co-administered Drug | Letermovir Regimen | Geometric Mean Ratio [90% CI] of Letermovir PK with/without Co-administered Drug (No Effect=1.00)
Co-administered Drug | Regimen of Co-administered Drug | Letermovir Regimen | AUC | Cmax | C24hr [C12hr for tacrolimus]
Antifungals
fluconazole | 400 mg single dose PO | 480 mg single dose PO | 1.11 (1.01, 1.23) | 1.06 (0.93, 1.21) | 1.28 (1.15, 1.43)
itraconazole | 200 mg once daily PO | 480 mg once daily PO | 1.33 (1.17, 1.51) | 1.21 (1.05, 1.39) | 1.90 (1.58, 2.28)
Antimycobacterials
rifampin | 600 mg single dose PO | 480 mg single dose PO | 2.03 (1.84, 2.26) | 1.59 (1.46, 1.74) | 2.01 (1.59, 2.54)
rifampin | 600 mg single dose IV | 480 mg single dose PO | 1.58 (1.38, 1.81) | 1.37 (1.16, 1.61) | 0.78 (0.65, 0.93)
rifampin | 600 mg once daily PO | 480 mg once daily PO | 0.81 (0.67, 0.98) | 1.01 (0.79, 1.28) | 0.14 (0.11, 0.19)
rifampin | 600 mg once daily PO (24 hours after rifampin) [These data are the effect of rifampin on letermovir 24 hours after final rifampin dose.] | 480 mg once daily PO | 0.15 (0.13, 0.17) | 0.27 (0.22, 0.31) | 0.09 (0.06, 0.12)
Immunosuppressants
cyclosporine | 200 mg single dose PO | 240 mg once daily PO | 2.11 (1.97, 2.26) | 1.48 (1.33, 1.65) | 2.06 (1.81, 2.35)
mycophenolate mofetil | 1 g single dose PO | 480 mg once daily PO | 1.18 (1.04, 1.32) | 1.11 (0.92, 1.34) | 1.39 (1.12, 1.74)
tacrolimus | 5 mg single dose PO | 80 mg twice daily PO | 1.02 (0.97, 1.07) | 0.92 (0.84, 1.00) | 1.02 (0.93, 1.12)
Abbreviations: PO= oral

Table 16: Drug Interactions: Changes in Pharmacokinetics for Co-administered Drug in the Presence of Letermovir
Co-administered Drug | Regimen of Co-administered Drug | Letermovir Regimen | Geometric Mean Ratio [90% CI] of Co-administered Drug PK with/without Letermovir (No Effect=1.00)
Co-administered Drug | Regimen of Co-administered Drug | Letermovir Regimen | AUC | Cmax | C24hr [C12hr reported for voriconazole.]
CYP3A Substrates
midazolam | 1 mg single dose IV | 240 mg once daily PO | 1.47 (1.37, 1.58) | 1.05 (0.94, 1.17) | 2.74 (2.16, 3.49)
midazolam | 2 mg single dose PO | 240 mg once daily PO | 2.25 (2.04, 2.48) | 1.72 (1.55, 1.92) | Not available
P-gp Substrates
digoxin | 0.5 mg single dose PO | 240 mg twice daily PO | 0.88 (0.80, 0.96) | 0.75 (0.63, 0.89) | 0.90 (0.84, 0.96)
Immunosuppressants
cyclosporine | 50 mg single dose PO | 240 mg once daily PO | 1.66 (1.51, 1.82) | 1.08 (0.97, 1.19) | 2.19 (1.80, 2.66)
mycophenolate mofetil | 1 g single dose PO | 480 mg once daily PO | 1.08 (0.97, 1.20) | 0.96 (0.82, 1.12) | 1.04 (0.86, 1.27)
tacrolimus | 5 mg single dose PO | 480 mg once daily PO | 2.42 (2.04, 2.88) | 1.57 (1.32, 1.86) | 2.53 (2.12, 3.03)
sirolimus | 2 mg single dose PO | 480 mg once daily PO | 3.40 (3.01, 3.85) | 2.76 (2.48, 3.06) | 3.15 (2.80, 3.55)
Antifungals and Antivirals
acyclovir | 400 mg single dose PO | 480 mg once daily PO | 1.02 (0.87, 1.2) | 0.82 (0.71, 0.93) | 1.13 (0.94, 1.36)
fluconazole | 400 mg single dose PO | 480 mg single dose PO | 1.03 (0.99, 1.08) | 0.95 (0.92, 0.99) | 1.04 (1.00, 1.08)
itraconazole | 200 mg once daily PO | 480 mg once daily PO | 0.76 (0.71, 0.81) | 0.84 (0.76, 0.92) | 0.67 (0.61, 0.73)
posaconazole | 300 mg single dose PO | 480 mg once daily PO | 0.98 (0.82, 1.17) | 1.11 (0.95, 1.29) | 1.10 (0.94, 1.30)
voriconazole | 200 mg twice daily PO | 480 mg once daily PO | 0.56 (0.51, 0.62) | 0.61 (0.53, 0.71) | 0.49 (0.42, 0.57)
HMG-CoA Reductase Inhibitors
atorvastatin | 20 mg single dose PO | 480 mg once daily PO | 3.29 (2.84, 3.82) | 2.17 (1.76, 2.67) | 3.62 (2.87, 4.55)
Oral Contraceptives
ethinyl estradiol (EE) /levonorgestrel (LNG) | 0.03 mg EE single dose PO | 480 mg once daily PO | 1.42 (1.32, 1.52) | 0.89 (0.83, 0.96) | 1.57 (1.45, 1.70)
ethinyl estradiol (EE) /levonorgestrel (LNG) | 0.15 mg LNG single dose PO | 480 mg once daily PO | 1.36 (1.30, 1.43) | 0.95 (0.86, 1.04) | 1.38 (1.32, 1.46)
Abbreviations: PO=oral

12.4 Microbiology

Mechanism of Action

Letermovir inhibits the CMV DNA terminase complex (pUL51, pUL56, and pUL89) which is required for viral DNA processing and packaging. Biochemical characterization and electron microscopy demonstrated that letermovir affects the production of proper unit length genomes and interferes with virion maturation. Genotypic characterization of virus resistant to letermovir confirmed that letermovir targets the terminase complex.

Antiviral Activity

The median EC50 value of letermovir against a collection of clinical CMV isolates in a cell-culture model of infection was 2.1 nM (range = 0.7 nM to 6.1 nM, n = 74). There was no significant difference in EC50 value by CMV gB genotype (gB1=29; gB2=27; gB3=11; and gB4=3).

Combination Antiviral Activity

No antagonism of the antiviral activity was seen when letermovir was combined with CMV DNA polymerase inhibitors (cidofovir, foscarnet, or ganciclovir).

Viral Resistance

In Cell Culture

CMV mutants with reduced susceptibility to letermovir have been selected in cell culture and the resistance mutations map to UL51, UL56, and UL89. Resistance-associated substitutions were found in pUL51 (P91S, A95V), pUL56 (C25F, S229F, V231A/L, N232Y, V236A/L/M, E237D, L241P, T244K/R, L254F, L257F/I, K258E, F261C/L/S, Y321C, C325F/R/W/Y, L328V, M329T, A365S, N368D, R369G/M/S), and pUL89 (N320H, D344E). EC50 values for recombinant CMV mutants expressing these substitutions are 1.6- to 9,300-fold higher than those for the wild-type reference virus.

In Clinical Studies

In a Phase 2b trial evaluating letermovir or placebo in 131 adult HSCT recipients, DNA sequence analysis of a select region of UL56 (amino acids 231 to 369) was performed on samples obtained from 12 letermovir-treated subjects who experienced prophylaxis failure and for whom on-treatment samples were available for analysis. One subject had a letermovir resistance substitution, pUL56 V236M (19-50-fold reduction in susceptibility).

In a Phase 3 trial (P001), DNA sequence analysis of the entire coding regions of UL56 and UL89 was performed on samples obtained from 50 letermovir-treated adult subjects who had received at least one dose of study drug and experienced prophylaxis failure and for whom samples were available for analysis. The pUL56 substitutions V236M (19-50-fold reduction), E237G (13-fold reduction), C325W (9300-fold reduction), and R369T (52-fold reduction) were detected in 3 subjects; however, no 2 subjects had substitutions at the same positions.

In a Phase 3 trial (P040), DNA sequence analysis of the entire coding regions of UL51, UL56 and UL89 was performed on samples obtained from 32 adult subjects (regardless of treatment group) who experienced prophylaxis failure or who discontinued early with CMV viremia. No letermovir resistance-associated substitutions were detected above the validated assay limit.

In a Phase 3 trial (P002), DNA sequence analysis of the entire coding regions of UL51, UL56 and UL89 was performed on samples obtained from 52 letermovir-treated adult subjects who experienced CMV disease or who discontinued early with CMV viremia. No previously characterized resistance-associated substitutions were identified. Novel substitutions were detected in letermovir-treated subjects at resistance-associated positions (pUL56 S229Y [2-fold reduction; n=1] and pUL56 M329I [0.77-fold reduction; n=9]) at low frequencies, ranging between 0.05 to 0.07.

In a Phase 2b trial (P030), DNA sequence analysis of the entire coding regions of UL51, UL56 and UL89 was performed on samples obtained from 10 letermovir-treated pediatric subjects at a visit for evaluation of CMV infection. A total of 2 letermovir resistance-associated substitutions both mapping to pUL56 were detected in 2 subjects. One subject had the substitution C325W (9300-fold reduction), and the other had R369S (38-fold reduction).

Cross Resistance

Cross resistance is not likely with drugs outside of this class. Letermovir is fully active against viral populations with substitutions conferring resistance to CMV DNA polymerase inhibitors (cidofovir, foscarnet, and ganciclovir). These DNA polymerase inhibitors are expected to be fully active against viral populations with substitutions conferring resistance to letermovir.

13 NONCLINICAL TOXICOLOGY

13.1 Carcinogenesis, Mutagenesis, Impairment of Fertility

Carcinogenesis and Mutagenesis

Letermovir was not genotoxic in in vitro or in vivo assays, including microbial mutagenesis assays, chromosomal aberration in Chinese hamster ovary cells, and in an in vivo mouse micronucleus study.

Letermovir was not carcinogenic in a 6-month RasH2 transgenic mouse study up to the highest doses tested (150 mg/kg/day in males and 300 mg/kg/day in females). Based on a comprehensive assessment of the available toxicology data and the CMV-specific target, letermovir is not expected to be carcinogenic in humans.

Impairment of Fertility

In a fertility and early embryonic development study in rats, no effects of letermovir on female fertility were observed at letermovir exposures (AUC) approximately 5 times higher than human exposure at the RHD.

In male rat fertility studies, decreased fertility associated with irreversible testicular toxicity was observed at ≥180 mg/kg/day (greater than or equal to 3 times the human exposure at the RHD). No fertility or testicular effects were observed at dose levels resulting in letermovir exposures (AUC) similar to human exposure at the RHD [see Nonclinical Toxicology (13.2)].

13.2 Animal Toxicology and/or Pharmacology

Testicular toxicity in rats observed at ≥180 mg/kg/day (greater than or equal to 3 times the human exposure at the RHD) was characterized by decreased testis weight, bilateral seminiferous tubular degeneration, decreased sperm count and motility, and resultant decreased male fertility. Male reproductive system toxicities were not observed in either a monkey testicular toxicity study up to 240 mg/kg/day (approximately 2 times higher than human exposure at the RHD), or a general toxicology study in mice up to 250 mg/kg/day (approximately 3 times higher than human exposure at the RHD).

The excipient, hydroxypropyl betadex, present in the IV letermovir formulation, has been associated with hearing loss resulting from damage to the inner ear in multiple animal species. In published studies in rats, a single subcutaneous dose of 2000 mg/kg hydroxypropyl betadex resulted in changes in hearing parameters and associated decreases in outer hair cells in the inner ear. These findings were observed at hydroxypropyl betadex levels approximately 3 times higher than those present in the letermovir IV drug product at the MRHD, based on body surface area (BSA) comparisons. No adverse changes in hearing parameters or hair cell populations in the inner ear were observed in rats following a single subcutaneous dose of 1000 mg/kg hydroxypropyl betadex, which corresponds to levels approximately 1.5 times higher than those present in the letermovir IV drug product at the MRHD, based on BSA comparisons [see Warnings and Precautions (5.2)].

14 CLINICAL STUDIES

14.1 Overview of Clinical Studies

An overview of the trials contributing to the assessment of efficacy and safety of PREVYMIS in HSCT and kidney transplant recipients is provided in Table 17.

Table 17: Trials Conducted with PREVYMIS
Trial (NCT Number) | Population | Trial Arms (N) [N represents the number of subjects treated.] | Duration of Prophylaxis Post-Transplant | Efficacy Endpoint
P001 (NCT02137772) | Adult allogeneic HSCT recipients [R+] | PREVYMIS (373) Placebo (192) | Through Week 14 | Clinically significant CMV infection through Week 24 post-HSCT
P040 (NCT03930615) | Adult allogeneic HSCT recipients [R+] at risk for late CMV infection and disease | PREVYMIS (144) Placebo (74) | Extension of prophylaxis from Week 14 through Week 28 | Clinically significant CMV infection through Week 28 post-HSCT
P002 (NCT03443869) | Adult kidney transplant recipients [D+/R-] | PREVYMIS (292) Valganciclovir (297) | Through Week 28 | CMV disease through Week 52 post-kidney transplant
P030 (NCT03940586) | Pediatric allogeneic HSCT recipients | PREVYMIS (63) | Through Week 14 | Clinically significant CMV infection through Week 24 post-HSCT

14.2 Adult CMV-seropositive Recipients [R+] of an Allogeneic Hematopoietic Stem Cell Transplant (Trial P001 and Trial P040)

Prophylaxis Through Week 14 (~100 days) Post-HSCT (Trial P001)

To evaluate PREVYMIS prophylaxis as a preventive strategy for CMV infection or disease in transplant recipients at high risk for CMV reactivation, the efficacy of PREVYMIS was assessed in a multicenter, double-blind, placebo-controlled Phase 3 Trial (P001, NCT02137772) in adult CMV-seropositive recipients [R+] of an allogeneic hematopoietic stem cell transplant (HSCT). Subjects were randomized (2:1) to receive either PREVYMIS at a dose of 480 mg once daily adjusted to 240 mg when co-administered with cyclosporine, or placebo. Randomization was stratified by investigational site and risk level for CMV reactivation at the time of study entry. Study drug was initiated after HSCT (at any time from Day 0 to Day 28 post-HSCT) and continued through Week 14 post-HSCT. Study drug was administered either orally or intravenously; the dose of PREVYMIS was the same regardless of the route of administration. Subjects received CMV DNA monitoring weekly until post-HSCT Week 14 and then bi-weekly until post-HSCT Week 24, with initiation of standard-of-care CMV pre-emptive therapy if CMV viremia was considered clinically significant. Subjects had continued follow-up through Week 48 post-HSCT.

Among the 565 treated subjects, 70 subjects were found to have CMV viremia prior to study drug initiation and were therefore excluded from the efficacy analyses. The efficacy population consisted of 325 subjects who received PREVYMIS (including 91 subjects who received at least one IV dose) and 170 who received placebo (including 41 subjects who received at least one IV dose). The IV formulation of PREVYMIS was used at investigators' discretion in subjects who were unable to take oral therapy (e.g., unable to tolerate oral intake). The median time to starting study drug was 8 days after transplantation. Thirty-four percent (34%) of subjects were engrafted at baseline. The median age was 55 years (range: 18 to 76 years). 57% were male; 84% were White; 9% were Asian; 2% were Black or African American; and 5% were other (American Indian or Alaska Native, multiple, and missing). 7% were Hispanic or Latino; 89% not Hispanic or Latino; and 4% other (not reported, unknown, and missing).

At baseline, 30% of all subjects had one or more of the following factors associated with increased risk for CMV reactivation (high risk stratum): Human Leukocyte Antigen (HLA)-related donor with at least one mismatch at one of the following three HLA-gene loci: HLA-A, -B or –DR; haploidentical donor; unrelated donor with at least one mismatch at one of the following four HLA-gene loci: HLA-A, -B, -C and -DRB1; use of umbilical cord blood as stem cell source; use of ex vivo T-cell-depleted grafts; Grade 2 or greater Graft-Versus-Host Disease (GVHD) requiring systemic corticosteroids. The remaining 70% of subjects did not meet any of these high risk stratum criteria and were therefore included in the low risk stratum. Additionally, 48% of subjects received a myeloablative regimen, 51% were receiving cyclosporine, and 43% were receiving tacrolimus. The most common primary reasons for transplant were acute myeloid leukemia (38%), myelodysplastic syndrome (16%), and lymphoma (12%).

Clinically Significant CMV Infection

The primary efficacy endpoint of Trial P001 was the incidence of clinically significant CMV infection through Week 24 post-HSCT (prophylaxis failure). Clinically significant CMV infection was defined as the occurrence of either CMV end-organ disease, or initiation of anti-CMV pre-emptive therapy (PET) based on documented CMV viremia (using the Roche COBAS® AmpliPrep/COBAS TaqMan® assay, LLoQ is 137 IU/mL, which is approximately 150 copies/mL) and the clinical condition of the subject. The protocol-specified guidance for CMV DNA thresholds for the initiation of PET during the treatment period was ≥ 150 copies/mL or > 300 copies/mL for subjects in the high and low risk strata, respectively. From Week 14 through Week 24, the threshold was >300 copies/mL for both high and low risk strata subjects. The Non-Completer=Failure (NC=F) approach was used, where subjects who discontinued from the trial prior to Week 24 post-HSCT or had a missing outcome at Week 24 post-HSCT were counted as failures.

Efficacy results from Trial P001 are shown in Table 18.

Table 18: Trial P001 Incidence of Clinically Significant CMV Infection in HSCT Recipients (NC=F Approach, FAS Population) Through Week 24
Parameter | PREVYMIS (N=325) | Placebo (N=170)
Proportion of subjects who failed prophylaxis | 38% | 61%
Reasons for failures [The categories of failure are mutually exclusive and based on the hierarchy of categories in the order listed.]
Clinically significant CMV infection by Week 24 [Through Week 14, 8% of subjects in the PREVYMIS group and 39% of subjects in the placebo group experienced clinically significant CMV infection.] | 18% | 42%
Initiation of PET based on documented CMV viremia | 16% | 40%
CMV end-organ disease | 2% | 2%
Discontinued from study before Week 24 [Reasons for discontinuation included adverse event, death, lost to follow-up, physician decision, and withdrawal by subject.] | 17% | 16%
Missing outcome in Week 24 visit window | 3% | 3%
Stratum-adjusted treatment difference (PREVYMIS-Placebo) [95% CI and p-value for the treatment differences in percent response were calculated using stratum-adjusted Mantel-Haenszel method with the difference weighted by the harmonic mean of sample size per arm for each stratum (high or low risk).]
Difference (95% CI) | -23.5 (-32.5, -14.6) [p-value <0.0001.]
Note: FAS=Full analysis set; FAS includes randomized subjects who received at least one dose of study medication, and excludes subjects with detectable CMV DNA at baseline. Approach to handling missing values: Non-Completer=Failure (NC=F) approach. With NC=F approach, failure was defined as all subjects who developed clinically significant CMV infection or prematurely discontinued from the study or had a missing outcome through Week 24 post-HSCT visit window.

Efficacy results were consistent across high and low risk strata for CMV reactivation. The time to clinically significant CMV infection is shown in Figure 1. Among subjects in the PREVYMIS group, the cumulative rate of clinically significant CMV infection increased from 6.8% at the end of prophylaxis (Week 14) to 18.9% at Week 24. In the placebo group, the cumulative rate of clinically significant CMV infection increased from 41.3% at Week 14 to 44.3% at Week 24 [see Dosage and Administration (2.2)].

Figure 1: P001: Kaplan-Meier Plot of Time to Onset of Clinically Significant CMV Infection Through Week 24 Post-Transplant in HSCT Recipients (FAS Population)

Post-hoc analysis demonstrated that among PREVYMIS-treated subjects, inclusion in the high risk stratum for CMV reactivation at baseline, occurrence of GVHD, and steroid use at any time after randomization may be associated with the development of clinically significant CMV infection between Week 14 and Week 24 post-HSCT.

Mortality

The Kaplan-Meier event rate for all-cause mortality in the PREVYMIS vs. placebo groups was 12% vs. 17% at Week 24 post-HSCT, and 24% vs. 28% at Week 48 post-HSCT.

Prophylaxis From Week 14 (~100 days) Through Week 28 (~200 days) Post-HSCT (Trial P040)

The efficacy of extending PREVYMIS prophylaxis from Week 14 (~100 days) through Week 28 (~200 days) post-HSCT in patients at risk for late CMV infection and disease was assessed in a multicenter, double-blind, placebo-controlled Phase 3 trial (P040, NCT03930615) in adult CMV-seropositive recipients [R+] of an allogeneic HSCT. Eligible subjects who completed PREVYMIS prophylaxis through ~100 days post-HSCT were randomized (2:1) to receive PREVYMIS or placebo from Week 14 through Week 28 post-HSCT. Subjects received PREVYMIS at a dose of 480 mg once daily (adjusted to 240 mg when co-administered with cyclosporine) or placebo. Study drug was administered either orally or IV; the dose of PREVYMIS was the same regardless of the route of administration. One subject received IV PREVYMIS for 2 days. Subjects were monitored through Week 28 post-HSCT for the primary efficacy endpoint with continued off-treatment follow-up through Week 48 post-HSCT.

Among the 218 treated subjects, 144 subjects received PREVYMIS and 74 received placebo. The median age was 55 years (range: 20 to 74 years); 62% were male; 79% were white; 11% were Asian; 2% were Black; 1% were multiple races; 6% had missing race; and 10% were Hispanic or Latino.

At study entry, all subjects had risk factors for late CMV infection and disease, with 64% having two or more risk factors. The risk factors included: HLA-related (sibling) donor with at least one mismatch at one of the following three HLA-gene loci: HLA-A, -B or –DR; haploidentical donor; unrelated donor with at least one mismatch at one of the following four HLA-gene loci: HLA-A, -B, -C and -DRB1; use of umbilical cord blood as stem cell source; use of ex vivo T-cell-depleted grafts; receipt of anti-thymocyte globulin; receipt of alemtuzumab; use of systemic prednisone (or equivalent) at a dose of ≥1 mg/kg of body weight per day. The most common reasons for transplant were acute myeloid leukemia (42%), acute lymphocytic leukemia (15%), and myelodysplastic syndrome (11%).

Clinically Significant CMV Infection

The primary efficacy endpoint of Trial P040 was the incidence of clinically significant CMV infection through Week 28 post-HSCT. Clinically significant CMV infection was defined as the occurrence of either CMV end-organ disease, or initiation of anti-CMV PET based on documented CMV viremia and the clinical condition of the subject. The Observed Failure (OF) approach was used, where subjects who discontinued prematurely from the study without viremia or were missing data at the timepoint were not counted as failures. The number of subjects who discontinued from the study before Week 28 without viremia was 14 (9.7%) in the PREVYMIS arm and 0 in the placebo arm. The number of subjects with a missing outcome in the Week 28 visit window was 3 (2.1%) in the PREVYMIS arm and 4 (5.4%) in the placebo arm, none had prior viremia.

Efficacy results from Trial P040 are shown in Table 19. Efficacy was consistent across subgroups based on participant characteristics (age, gender, race) and risk factors for late CMV infection and disease.

Table 19: Trial P040 Efficacy Results in HSCT Recipients at Risk for Late CMV Infection and Disease (OF Approach, FAS Population)
Parameter | PREVYMIS (~200 days PREVYMIS) (N=144) | Placebo (~100 days PREVYMIS) (N=74)
Failures [The categories of failure are mutually exclusive and based on the hierarchy of categories in the order listed.] | 2.8% | 18.9%
Clinically significant CMV infection from Week 14 through Week 28 [Clinically significant CMV infection was defined as CMV end-organ disease (proven or probable) or initiation of PET based on documented CMV viremia and the clinical condition of the subject.] | 1.4% | 17.6%
Initiation of PET based on documented CMV viremia | 0.7% | 14.9%
CMV end-organ disease | 0.7% | 2.7%
Discontinued from study with CMV viremia before Week 28 | 1.4% | 1.4%
Stratum-adjusted treatment difference (PREVYMIS (~200 days PREVYMIS)-Placebo (~100 days PREVYMIS)) [The 95% CIs and p-value for the treatment differences in percent response were calculated using stratum-adjusted Mantel-Haenszel method with the difference weighted by the harmonic mean of sample size per arm for each stratum (haploidentical donor yes or no). A one-sided p-value ≤0.0249 was used for declaring statistical significance.]
Difference (95% CI) | -16.1 (-25.8, -6.5) [p-value = 0.0005]
Approach to handling missing values: Observed Failure (OF) approach. With the OF approach, failure was defined as all subjects who developed clinically significant CMV infection or discontinued prematurely from the study with CMV viremia from Week 14 (~100 days) through Week 28 (~200 days) post-HSCT.
N = Number of subjects in each treatment group.

The time to clinically significant CMV infection is shown in Figure 2. Among subjects in the PREVYMIS group, the cumulative rate of clinically significant CMV infection increased from 1.6% at the end of prophylaxis (Week 28) to 15.6% at Week 38. In the placebo group, the cumulative rate of clinically significant CMV infection increased from 17.6% at Week 28 to 19.0% at Week 38. There were no additional cases of clinically significant CMV infection in either group between Weeks 38 and 48 [see Dosage and Administration (2.2)].

Figure 2: Trial P040 Kaplan-Meier Plot of Time to Onset of Clinically Significant CMV Infection From Week 14 Through Week 48 Post-transplant in HSCT Recipients at Risk for Late CMV Infection and Disease (FAS Population)

14.3 Adult CMV-seronegative Recipients of a Kidney Transplant from a CMV-seropositive Donor [D+/R-] (Trial P002)

To evaluate PREVYMIS prophylaxis as a preventive strategy for CMV disease in kidney transplant recipients, the efficacy of PREVYMIS was assessed in a multicenter, double-blind, active comparator-controlled non-inferiority Phase 3 trial (P002, NCT03443869) in adult kidney transplant recipients at high risk [D+/R-]. Subjects were randomized (1:1) to receive either PREVYMIS or valganciclovir. PREVYMIS was administered at a dose of 480 mg once daily (adjusted to 240 mg when co-administered with cyclosporine). PREVYMIS was given concomitantly with acyclovir. Valganciclovir was given concomitantly with a placebo to acyclovir. Randomization was stratified by the use or nonuse of highly cytolytic, anti-lymphocyte immunotherapy during induction. Study drug was initiated between Day 0 and Day 7 post-kidney transplant and continued through Week 28 (~200 days) post-transplant. Study drug was administered either orally or IV; the dose of PREVYMIS was the same regardless of the route of administration. Three subjects received IV PREVYMIS for a mean duration of 1.7 days. Subjects were monitored through Week 52 post-transplant.

Among the 589 treated subjects, 292 subjects received PREVYMIS and 297 received valganciclovir. The median age was 51 years (range: 18 to 82 years); 72% were male; 84% were White; 9% were Black; 3% were multiple; 2% were Asian; 1% Alaskan native or American Indian; 17% were Hispanic or Latino; and 60% received a kidney from a deceased donor. The most common primary reasons for transplant were congenital cystic kidney disease (17%), hypertension (16%), and diabetes/diabetic nephropathy (14%).

CMV Disease

The primary efficacy endpoint of Trial P002 was the incidence of CMV disease (CMV end-organ disease or CMV syndrome, confirmed by an independent adjudication committee) through Week 52 post-transplant. The Observed Failure (OF) approach was used, where subjects who discontinued prematurely from the study for any reason or were missing data at the timepoint were not counted as failures. The number of subjects who discontinued from the study before Week 52 was 32 (11%) in the PREVYMIS arm and 28 (9%) in the valganciclovir arm. The number of subjects with a missing outcome in the Week 52 visit window was 24 (8%) in the PREVYMIS arm and 25 (8%) in the valganciclovir arm.

Efficacy results from Trial P002 are shown in Table 20.

Table 20: Trial P002 Incidence of CMV Disease in Kidney Transplant Recipients (OF Approach, FAS Population) Through Week 52
Parameter | PREVYMIS (N=289) | Valganciclovir (N=297)
CMV Disease [CMV disease cases confirmed by an independent adjudication committee.] Through Week 52 | 10% | 12%
CMV Syndrome [Defined as evidence of CMV in blood by viral isolation, rapid culture, antigenemia, or nucleic acid testing, and two or more of the following: 1) fever ≥38°C for at least 2 days, 2) new or increased malaise/fatigue, 3) leukopenia or neutropenia on two separate measurements at least 24 hours apart, 4) ≥5% atypical lymphocytes, 5) thrombocytopenia, 6) elevation of ALT or AST to 2x ULN.] | 8% | 11%
CMV End-organ Disease | 2% | <1%
Stratum-adjusted Treatment Difference [The 95% CIs for the treatment differences in percent response were calculated using stratum-adjusted Mantel- Haenszel method with the difference weighted by the harmonic mean of sample size per arm for each stratum (use/non-use of highly cytolytic, anti-lymphocyte immunotherapy during induction).] (PREVYMIS – Valganciclovir) | -1.4 (-6.5, 3.8) [Based on a non-inferiority margin of 10%, PREVYMIS is non-inferior to valganciclovir.]
Note: Approach to handling missing values: Observed failure (OF) approach. With OF approach, subjects who discontinued from the study before Week 52 or had a missing outcome in the Week 52 visit window were not counted as failures.

Efficacy was comparable across all subgroups, including the use/nonuse of highly cytolytic, anti-lymphocyte immunotherapy during induction.

In an exploratory analysis of the incidence of CMV disease through Week 28 post-transplant, the difference (PREVYMIS – Valganciclovir) was -1.7% with 95% CI of (-3.4, 0.1). No subjects in the PREVYMIS group experienced CMV disease through Week 28 post-transplant (end of treatment period) compared with 5 subjects in the valganciclovir group.

14.4 Pediatric Recipients of an Allogeneic HSCT (Trial P030)

Sixty-three children 2 months to less than 18 years of age who had an allogeneic HSCT were enrolled in a multicenter, open-label, single-arm pharmacokinetic, safety and effectiveness study of PREVYMIS (P030, NCT03940586). Subjects received PREVYMIS daily either orally or intravenously for CMV prophylaxis within 28 days post-HSCT through Week 14 post-HSCT. The intravenous formulation was used for up to four weeks in subjects who were unable to take oral therapy. The daily doses of PREVYMIS were based on body weight [see Dosage and Administration (2.3, 2.5)]. Among the 63 treated subjects, 8 were 2 months to less than 2 years of age, 27 were 2 to less than 12 years of age and 28 were 12 to less than 18 years of age. The median age was 11 years; 70% were male; 70% were White; 14% were Asian; 5% were Black; and 22% were Hispanic or Latino [see Use in Specific Populations (8.4)].

The efficacy analyses population consisted of 56 subjects who received at least one dose of study drug and had no detectable CMV DNA at baseline. The proportion of subjects who failed CMV prophylaxis through Week 24 post-HSCT was 25% (14 of the 56 subjects). Six subjects had initiation of pre-emptive therapy based on CMV viremia and 8 subjects discontinued from the study before Week 24. None of the subjects had CMV end-organ disease.

PREVYMIS is indicated for pediatric recipients of an allogeneic HSCT aged 6 months and older and weighing at least 6 kg.

16 HOW SUPPLIED/STORAGE AND HANDLING

Tablets:

Each PREVYMIS 240 mg tablet is a yellow oval tablet; each tablet is debossed with "591" on one side and corporate logo on the other side. Each PREVYMIS 480 mg tablet is a pink oval, bi-convex tablet debossed with "595" on one side and corporate logo on the other side.

The 240 mg tablets are packaged into a carton (NDC 0006-3075-02) containing four (4) Child Resistant (CR) Dosepaks®, each containing a 7-count blister card for a total of 28 tablets, or into a carton (NDC 0006-3075-04) containing two (2) unit-dose 7-count blister cards for a total of 14 tablets.

The 480 mg tablets are packaged into a carton (NDC 0006-3076-02) containing four (4) Child Resistant (CR) Dosepaks®, each containing a 7-count blister card for a total of 28 tablets, or into a carton (NDC 0006-3076-04) containing two (2) unit-dose 7-count blister cards for a total of 14 tablets.

STORAGE AND HANDLING

Store PREVYMIS tablets in the original package until use to protect from moisture.

Store PREVYMIS tablets at 20°C to 25°C (68°F to 77°F); excursions permitted to 15°C to 30°C (59°F to 86°F) [see USP Controlled Room Temperature].

Oral Pellets:

PREVYMIS oral pellets are supplied as beige round pellets in packets. Each packet contains 20 mg of letermovir.

PREVYMIS oral pellets are supplied as beige round pellets in packets. Each packet contains 120 mg of letermovir.

The 20 mg packets of PREVYMIS oral pellets are packaged into a carton (NDC 0006-5086-01). Each carton contains 30 child resistant packets.

The 120 mg packets of PREVYMIS oral pellets are packaged into a carton (NDC 0006-5085-01). Each carton contains 30 child resistant packets.

Store PREVYMIS oral pellets in the original packet until use.

Store PREVYMIS oral pellets at 20°C to 25°C (68°F to 77°F); excursions permitted between 15°C to 30°C (59°F to 86°F) [see USP Controlled Room Temperature].

Injection:

PREVYMIS is supplied as a sterile, clear and colorless solution for intravenous use of 240 mg/12 mL (20 mg/mL) or 480 mg/24 mL (20 mg/mL) that may contain a few product-related small translucent or white particles.

The single-dose vials are supplied in cartons that contain a 240 mg single-dose vial (NDC 0006-5003-01) or a 480 mg single-dose vial (NDC 0006-5004-01).

STORAGE AND HANDLING

Store PREVYMIS injection vials at 20°C to 25°C (68°F to 77°F); excursions permitted to 15°C to 30°C (59°F to 86°F) [see USP Controlled Room Temperature].

Store in the original carton to protect from exposure to light.

17 PATIENT COUNSELING INFORMATION

Advise the patient to read the FDA-approved patient labeling (Patient Information and Instructions for Use).

Drug Interactions

Inform patients that PREVYMIS may interact with some drugs; therefore, advise patients to report the use of any prescription, non-prescription medication, or herbal products to their healthcare provider [see Dosage and Administration (2.4, 2.6), Contraindications (4), Warnings and Precautions (5.1), and Drug Interactions (7)].

Risks Associated with Hydroxypropyl Betadex Excipient in Intravenous Formulation

Inform patients that the intravenous formulation of PREVYMIS contains hydroxypropyl betadex which is eliminated through glomerular filtration and may accumulate in patients with renal impairment. In animals, hydroxypropyl betadex has been shown to cause ototoxicity [see Warnings and Precautions (5.2), Use in Specific Populations (8.6) and Nonclinical Toxicology (13.2)].

Administration

Inform patients that it is important not to miss or skip doses and to take PREVYMIS for the duration that is recommended by the healthcare provider. Instruct patients that if they miss a dose of PREVYMIS, they should take it as soon as they remember. If they do not remember until it is time for the next dose, instruct them to skip the missed dose and go back to the regular schedule. Instruct patients not to double their next dose or take more than the prescribed dose.

Advise patients that PREVYMIS injection should be used only in patients unable to take oral therapy and that patients should be switched to oral therapy as soon as they are able [see Dosage and Administration (2.1)].

For PREVYMIS oral pellets, advise patients or caregivers to read and follow the Instructions for Use for preparing and taking the correct dose [see Dosage and Administration (2.3, 2.4, 2.5, 2.6, 2.9)].

Storage

Advise patients to store PREVYMIS tablets and oral pellets in the original package until use [see How Supplied/Storage and Handling (16)].

Distributed by: Merck Sharp & Dohme LLC
Rahway, NJ 07065, USA

For patent information: www.msd.com/research/patent

The trademarks depicted herein are owned by their respective companies.

Copyright © 2017-2026 Merck & Co., Inc., Rahway, NJ, USA, and its affiliates.
All rights reserved.

uspi-mk8228-mf-2601r012

Patient Information
PREVYMIS® (PREH-vih-miss) (letermovir) tablets | PREVYMIS® (PREH-vih-miss) (letermovir) oral pellets | PREVYMIS® (PREH-vih-miss) (letermovir) injection, for intravenous use

What is PREVYMIS?

PREVYMIS is a prescription medicine used to help prevent:

- cytomegalovirus (CMV) infection and disease in adults and children 6 months and older weighing at least 13.2 pounds (lbs) or 6 kilograms (kg) who:
  - have received an allogeneic hematopoietic stem cell (bone marrow) transplant, and
  - have a high risk for getting CMV infection and disease.
- CMV disease in adults and children 12 years of age and older weighing at least 88.2 lbs (40 kg) who:
  - have received a kidney transplant, and
  - have a high risk for getting CMV disease.

It is not known if PREVYMIS is safe and effective in:

- children under 6 months of age or weighing less than 13.2 lbs (6 kg) who received a hematopoietic stem cell transplant, or
- children under 12 years of age or weighing less than 88.2 lbs (40 kg) who received a kidney transplant.

Who should not take PREVYMIS?

Do not take PREVYMIS if you take:

- pimozide
- ergot alkaloids

If you are taking PREVYMIS with cyclosporine, do not take:

- pitavastatin or simvastatin

What should I tell my healthcare provider before taking PREVYMIS?

Before taking PREVYMIS, tell your healthcare provider about all your medical conditions, including if you:

- have kidney or liver problems.
- are pregnant or plan to become pregnant. It is not known if PREVYMIS will harm your unborn baby.
- are breastfeeding or plan to breastfeed. It is not known if PREVYMIS passes into your breast milk. Talk to your healthcare provider about the best way to feed your baby while taking PREVYMIS.

Tell your healthcare provider about all of the medicines you take, including prescription and over-the-counter medicines, vitamins and herbal supplements. PREVYMIS may affect the way other medicines work, and other medicines may affect how PREVYMIS works and cause serious side effects.

Know the medicines you take. Keep a list of medicines and show it to your healthcare provider and pharmacist when you get a new medicine. Your healthcare provider or pharmacist will tell you if it is safe to take PREVYMIS with other medicines. Do not start or stop taking another medicine without telling your healthcare provider first.

How should I take PREVYMIS?

- PREVYMIS comes as a tablet, oral pellets, or can be given by your healthcare provider through an IV line (intravenously).
- PREVYMIS given intravenously should be used only if you are unable to take PREVYMIS tablets or PREVYMIS oral pellets. You should switch to PREVYMIS tablets or PREVYMIS oral pellets as soon as you are able to.
- Take PREVYMIS tablets or oral pellets exactly as your healthcare provider tells you to take it. Do not stop taking PREVYMIS without talking to your healthcare provider first.
- Take PREVYMIS tablets or oral pellets 1 time a day.
- It is important that you do not miss or skip doses of PREVYMIS.
- If you miss a dose of PREVYMIS tablets or oral pellets, take it as soon as you remember. If you do not remember until it is time for your next dose, skip the missed dose and take your dose at the next scheduled time. Do not take 2 doses of PREVYMIS at the same time or take more than your prescribed dose to make up for a missed dose.
- If you take too much PREVYMIS tablets or oral pellets, call your healthcare provider right away.

- If you take PREVYMIS tablets:
  - Take PREVYMIS with or without food.
  - Swallow PREVYMIS tablets whole.
- If you take PREVYMIS oral pellets:
  - Your healthcare provider will tell you the number of PREVYMIS oral pellet packets to take for your prescribed dose.
  - PREVYMIS oral pellets can be taken by mouth after mixing with soft food or given through a nasogastric tube (NG tube) or gastric tube (G tube).
  - See the Instructions for Use for the right way to prepare and take a dose of PREVYMIS oral pellets. Keep the Instructions for Use and follow it each time you prepare and take PREVYMIS oral pellets.
  - Do not crush or chew PREVYMIS oral pellets.
- If you receive PREVYMIS through an IV line (intravenously):
  - You will receive PREVYMIS 1 time each day given over 1 hour.
  - If you miss or skip your dose of PREVYMIS, call your healthcare provider right away.

What are the possible side effects of PREVYMIS?

The most common side effects of PREVYMIS in adults who have received a hematopoietic stem cell transplant include:

- nausea
- diarrhea
- vomiting
- swelling in your arms and legs

- cough
- headache
- tiredness
- stomach (abdominal) pain

The most common side effect of PREVYMIS in adults who have received a kidney transplant is diarrhea.

The side effects of PREVYMIS in children are similar to the side effects in adults.

These are not all the possible side effects of PREVYMIS.

Call your doctor for medical advice about side effects. You may report side effects to FDA at 1-800-FDA-1088.

How should I store PREVYMIS?

- Store PREVYMIS tablets, PREVYMIS oral pellets, and PREVYMIS injection at room temperature between 68°F to 77°F (20°C to 25°C).
- Store PREVYMIS tablets in the original package until you are ready to take it to protect from moisture.
- Store PREVYMIS oral pellets in the original packet until you are ready to take them.
- Store PREVYMIS injection in the original carton to protect from exposure to light.

Keep PREVYMIS and all medicines out of the reach of children.

General information about the safe and effective use of PREVYMIS.

Medicines are sometimes prescribed for purposes other than those listed in the Patient Information leaflet. Do not use PREVYMIS for a condition for which it was not prescribed. Do not give PREVYMIS to other people, even if they have the same symptoms that you have. It may harm them. You can ask your pharmacist or healthcare provider for information about PREVYMIS that is written for healthcare professionals.

What are the ingredients in PREVYMIS?

Active ingredient: letermovir

Inactive ingredients:

Tablets: colloidal silicon dioxide, croscarmellose sodium, magnesium stearate, microcrystalline cellulose, and povidone 25.

Film coating: hypromellose 2910, iron oxide red (only for 480 mg tablets), iron oxide yellow, lactose monohydrate, titanium dioxide, and triacetin. Carnauba wax is added as a polishing agent.

Oral Pellets: colloidal silicon dioxide, croscarmellose sodium, magnesium stearate, microcrystalline cellulose, and povidone K-29/32.

Film coating: hypromellose 2910, iron oxide red, iron oxide yellow, lactose monohydrate, titanium dioxide, and triacetin.

Injection: hydroxypropyl betadex, sodium chloride, sodium hydroxide, and Water for Injection.

Distributed by: Merck Sharp & Dohme LLC
Rahway, NJ 07065, USA

For patent information: http://www.msd.com/research/patent
The trademarks depicted herein are owned by their respective companies.
Copyright © 2017-2024 Merck & Co., Inc., Rahway, NJ, USA, and its affiliates.
All rights reserved.
usppi-mk8228-mf-2408r004

For more information go to www.PREVYMIS.com or call 1-800-444-2080.

This Patient Information has been approved by the U.S. Food and Drug Administration. Revised: 08/2024

INSTRUCTIONS FOR USE

Important: Read this booklet first
INSTRUCTIONS FOR USE
PREVYMIS® [PREH-vih-miss]
(letermovir)
oral pellets
This Instructions for Use contains information
on how to take PREVYMIS oral pellets.

Table of Contents

- Important information you need to know before taking PREVYMIS oral pellets
- Taking PREVYMIS oral pellets
  - Mixing PREVYMIS oral pellets with soft food
  - Giving PREVYMIS oral pellets through a gastric tube (G tube) or nasogastric tube (NG tube)
- Storing PREVYMIS oral pellets packets
- Learn more about PREVYMIS oral pellets

Important information you need to know before taking PREVYMIS oral pellets

- Take PREVYMIS oral pellets exactly as instructed by your healthcare provider.
- Take PREVYMIS oral pellets 1 time a day.
- Your healthcare provider will tell you the number of PREVYMIS oral pellets packets to take for your prescribed dose.
- Make sure you take your entire dose of PREVYMIS oral pellets each time.
- Do not crush or chew PREVYMIS oral pellets.
- Do not miss or skip doses of PREVYMIS oral pellets.
- If you miss a dose of PREVYMIS oral pellets, take it as soon as you remember. If you do not remember until it is time for your next dose, skip the missed dose and take your dose at the next scheduled time. Do not take 2 doses of PREVYMIS oral pellets at the same time or take more than your prescribed dose to make up for a missed dose.
- If you take too much PREVYMIS oral pellets, call your healthcare provider right away.

Taking PREVYMIS oral pellets
PREVYMIS oral pellets can be taken by mouth after mixing with soft food or given through a gastric tube (G tube) or nasogastric tube (NG tube). Talk to your healthcare provider about which way to take PREVYMIS oral pellets.
Follow 1 of these ways to take PREVYMIS oral pellets:

- Mix PREVYMIS oral pellets with soft food and take by mouth – go to page 5.
- Give PREVYMIS oral pellets through a gastric tube (G tube) or nasogastric tube (NG tube) – go to page 13.

Mixing PREVYMIS oral pellets with soft food
Important information about mixing PREVYMIS oral pellets with soft food

- You can mix PREVYMIS oral pellets with soft food (such as applesauce, yogurt, or pudding) that is at or below room temperature.
  - Do not use hot food.

- You must take all of the PREVYMIS oral pellets mixture within 10 minutes of mixing PREVYMIS oral pellets with the soft food.
- Throw away the PREVYMIS oral pellets mixed with soft food if you do not take it within 10 minutes, and prepare a new dose.

Step 1: Wash your hands with soap and water. Dry your hands.

Step 2: Check the expiration date located on the top of the carton.

- Do not use if PREVYMIS oral pellets is expired.

Step 3: Check the pharmacy label for the number of PREVYMIS oral pellets packets needed for your dose.

Step 4: Gather all of your supplies on a clean surface:

- the number of packets according to Step 3
- scissors
- small bowl
- teaspoon (small spoon)

Step 5: Pick a soft food that you enjoy (such as applesauce, yogurt, or pudding).

- Soft food should be at or below room temperature.
- Do not use hot food.

Step 6: Put 1 to 3 teaspoons (small spoons) of soft food into the small bowl.

Step 7: Tap the packets to loosen the pellets to the bottom of the packets.

- Hold the packets with the dotted line at the top.

Step 8: Cut open the packets with scissors at the dotted line.

Step 9: Lightly tap the packets to carefully sprinkle all of the PREVYMIS oral pellets onto the soft food in the same small bowl.

- Make sure all of the pellets go into the small bowl.
- Make sure the packets are empty.

Step 10: Use the teaspoon to gently mix the food and PREVYMIS oral pellets together.

Step 11: Take or give all of the PREVYMIS oral pellets mixture.

- When finished, check to make sure that no PREVYMIS oral pellets are left in the bowl or on the teaspoon.
- If there are PREVYMIS oral pellets left in the bowl or on the teaspoon, add more soft food, mix, and take or give the remaining mixture.
- If you are hungry, you can eat more food or a meal afterwards.

Take or give all of the PREVYMIS oral pellets mixture within 10 minutes of mixing PREVYMIS oral pellets with the soft food.
Throw away the PREVYMIS oral pellets mixed with soft food if you do not take it within 10 minutes, and prepare a new dose.

Step 12: Cleaning up

- Throw the empty packets into the trash.
- Wash the small bowl and teaspoon with soap and water.
- Put everything in a clean, dry place.

Go to page 28 for Storing PREVYMIS oral pellets packets and page 32 to Learn more about PREVYMIS oral pellets.

Giving PREVYMIS oral pellets through a gastric tube (G tube) or nasogastric tube (NG tube)
These instructions are for giving PREVYMIS oral pellets through a G tube or NG tube.

Gastric tube
(G tube)

Nasogastric tube
(NG tube)

Ask your healthcare provider how to give PREVYMIS oral pellets through a G tube or NG tube and how to clean the G tube or NG tube.
Ask your healthcare provider how to flush the G tube or NG tube before taking or giving a dose of PREVYMIS oral pellets.

- Your healthcare provider will tell you how much water to use.

Giving PREVYMIS oral pellets through a G tube or NG tube
Important information you need to know before mixing PREVYMIS oral pellets with water

- Mix PREVYMIS oral pellets with room temperature water.
  - Do not mix PREVYMIS oral pellets with hot or cold (refrigerated) water.
  - After you mix PREVYMIS oral pellets with room temperature water, you must wait at least 10 minutes before giving it. This allows the PREVYMIS oral pellets to become loose or broken up.
  - After 10 minutes, give the PREVYMIS oral pellets mixture through the G tube or NG tube.
  - If you do not give the PREVYMIS oral pellets mixture within 2 hours, throw away the PREVYMIS oral pellets mixture and start over.

Step 1: Wash your hands with soap and water. Dry your hands.

Step 2: Check the expiration date located on the top of the carton.

- Do not use if PREVYMIS oral pellets is expired.

Step 3: Check the pharmacy label for the number of PREVYMIS oral pellets packets needed for your dose.

Step 4: Gather all your supplies on a clean surface:

- the number of PREVYMIS oral pellets packets according to Step 3
- scissors
- clock or timer
- small glass
- syringe provided by your healthcare provider or pharmacist
- medicine cup (15 to 30 mL) provided by your healthcare provider or pharmacist

Step 5: Pour a small amount of room temperature water into the small glass.

- Do not use hot or cold (refrigerated) liquid.

Step 6: Place the tip of the syringe into the small glass of room temperature water. Pull up on the syringe plunger to measure the amount of water needed for your dose.

- Your healthcare provider will tell you how much water you need for your dose.

Step 7: Add the water to the medicine cup by holding the barrel of the syringe and pushing the syringe plunger all the way down.

Step 8: Tap the packets to loosen the pellets to the bottom of the packets.

- Hold the packets with the dotted line at the top.

Step 9: Cut open the packets with scissors at the dotted line.

Step 10: Lightly tap the packets to carefully pour the PREVYMIS oral pellets into the same medicine cup.

- Make sure all of the PREVYMIS oral pellets go into the medicine cup.
- Make sure the packets are empty.

Step 11: Use a clock or timer and wait 10 minutes.

- Do not shake or swirl the medicine cup.

Important: While waiting, keep the medicine cup in a safe place out of reach of children.

- PREVYMIS oral pellets will not dissolve but will become loose or broken up.
- After 10 minutes, the PREVYMIS oral pellets mixture will be ready to use.
- Follow Steps 12-19 to give the PREVYMIS oral pellets mixture through the G tube or NG tube.

Step 12: Gently stir the PREVYMIS oral pellets mixture with the syringe tip.

- Do not shake or swirl the medicine cup.

Step 13: Tilt the medicine cup and pull up on the syringe plunger to draw up all of the PREVYMIS oral pellets mixture from the medicine cup. Give the PREVYMIS oral pellets mixture right away after it is drawn up into the syringe.

Step 14: Give the PREVYMIS oral pellets mixture.

- Gently turn the syringe upside down (invert) to keep the medicine from settling.
  - Do not shake the syringe since this can cause air bubbles.
- Attach the syringe to the G tube or NG tube.
- Slowly push on the plunger to move the mixture through the G tube or NG tube.

Step 15: Use the same syringe to withdraw more water from the small glass.

- Your healthcare provider will tell you how much water to use to rinse the G tube or NG tube.

Step 16: Slowly push the syringe plunger all the way down to add the water in the syringe into the same medicine cup.

Step 17: Gently stir the rinse mixture with the syringe tip.

- Do not shake or swirl the medicine cup.

Step 18: Tilt the medicine cup and pull up on the syringe plunger to draw up all of the rinse mixture from the medicine cup.

Step 19: Give the rinse mixture.

- Gently turn the syringe upside down (invert) to keep the medicine from settling.
  - Do not shake the syringe since this can cause air bubbles.
- Attach the syringe to the G tube or NG tube.
- Slowly push the plunger all the way down to move the rinse mixture through the G tube or NG tube.

Step 20: Flush the G tube or NG tube right away using water.

- Ask your healthcare provider how much water to use.

Step 21: Cleaning up

- Throw the empty packets into the trash.
- Hand wash the syringe and medicine cup with warm water and dish soap.
  - Do not wash the syringe and medicine cup in the dishwasher.
  - Do not boil the syringe and medicine cup.
- Put everything in a clean, dry place.

Go to page 28 for Storing PREVYMIS oral pellets packets and page 32 to Learn more about PREVYMIS oral pellets.

Storing PREVYMIS oral pellets packets

- Store PREVYMIS oral pellets at room temperature between 68°F to 77°F (20°C to 25°C).
- Store PREVYMIS oral pellets in the original packet until you are ready to take them.
- Keep PREVYMIS oral pellets and all medicine out of the reach of children.

Learn more about PREVYMIS oral pellets

For more information on how to use PREVYMIS oral pellets, ask your healthcare provider or pharmacist and read the PREVYMIS Patient Information.

For more information about PREVYMIS oral pellets, go to PREVYMIS.com or call 1-800-444-2080.

Distributed by:
Merck Sharp & Dohme LLC
Rahway, NJ 07065, USA

Copyright © 2024 Merck & Co., Inc., Rahway, NJ, USA, and its affiliates. All rights reserved.

usifu-mk8228-op-2408r000

This Instructions for Use has been approved by the U.S. Food and Drug Administration.

Approved: 08/2024

PRINCIPAL DISPLAY PANEL - 240 mg Tablet Dose Pack Carton

NDC 0006-3075-02

PREVYMIS®
(letermovir) tablets

240 mg per tablet

Rx only

28 Tablets

This carton contains a total of 28 tablets
packaged within 4 dose packs.
Each dose pack contains 7 blister units
with one tablet per blister unit.

PRINCIPAL DISPLAY PANEL - 240 mg Tablet Blister Carton

NDC 0006-3075-04

Prevymis®
(letermovir) tablets

240 mg

Each tablet contains 240 mg letermovir.

This is a bulk package and not intended for dispensing.
This package is not child resistant.

Rx only

14 tablets: 7 tablets x 2 blister cards

PRINCIPAL DISPLAY PANEL - 480 mg Tablet Dose Pack Carton

NDC 0006-3076-02

PREVYMIS®
(letermovir) tablets

480 mg per tablet

1 tablet a day
28-day supply

Rx only

28 Tablets

This carton contains a total of 28 tablets
packaged within 4 dose packs.
Each dose pack contains 7 blister units
with one tablet per blister unit.

PRINCIPAL DISPLAY PANEL - 480 mg Tablet Blister Carton

NDC 0006-3076-04

Prevymis®
(letermovir) tablets

480 mg

Each tablet contains 480 mg letermovir.

This is a bulk package and not intended for dispensing.
This package is not child resistant.

Rx only

14 tablets: 7 tablets x 2 blister cards

PRINCIPAL DISPLAY PANEL - 12 mL Vial Carton

NDC 0006-5003-01

Prevymis®
(letermovir) Injection

240 mg / 12 mL
(20 mg/mL)

For Intravenous Infusion Only

Requires dilution prior to administration.
Use a 0.2 or 0.22 micron in-line filter
during infusion.
See Package Insert.

Rx only

Single-dose vial. Discard unused portion.

PRINCIPAL DISPLAY PANEL - 24 mL Vial Carton

NDC 0006-5004-01

Prevymis®
(letermovir) Injection

480 mg /24 mL
(20 mg/mL)

For Intravenous Infusion Only

Requires dilution prior to administration.
Use a 0.2 or 0.22 micron in-line filter
during infusion.
See Package Insert.

Rx only

Single-dose vial. Discard unused portion.

PRINCIPAL DISPLAY PANEL - 20 mg Oral Pellets Carton

NDC 0006-5086-01

PREVYMIS®

(letermovir) oral pellets

20 mg per packet

Each packet contains 20 mg letermovir.

DIRECTIONS FOR USE: See enclosed
Instructions for Use booklet and
prescribing information.

Rx only

30 packets

PRINCIPAL DISPLAY PANEL - 120 mg Oral Pellets Carton

NDC 0006-5085-01

PREVYMIS®

(letermovir) oral pellets

120 mg per packet

Each packet contains 120 mg letermovir

DIRECTIONS FOR USE: See enclosed
Instructions for Use booklet and
prescribing information.

Rx only

30 packets